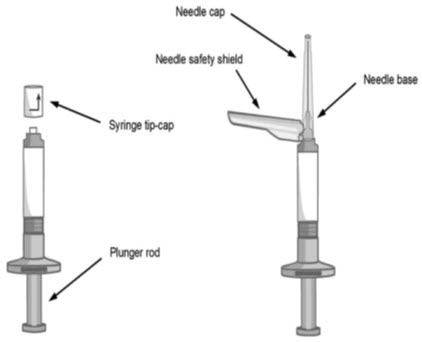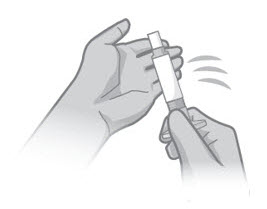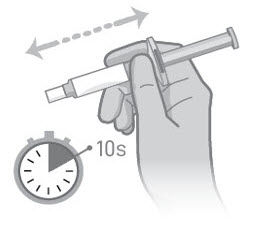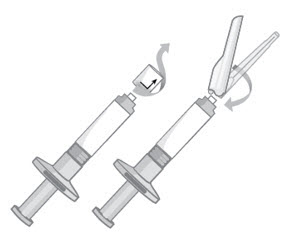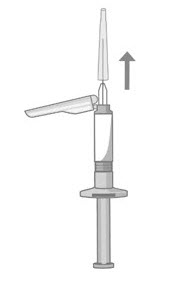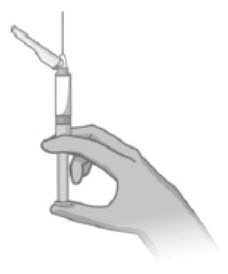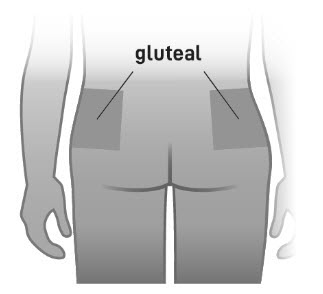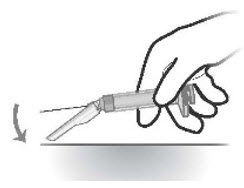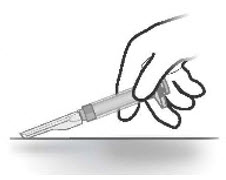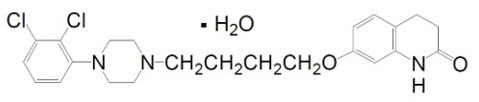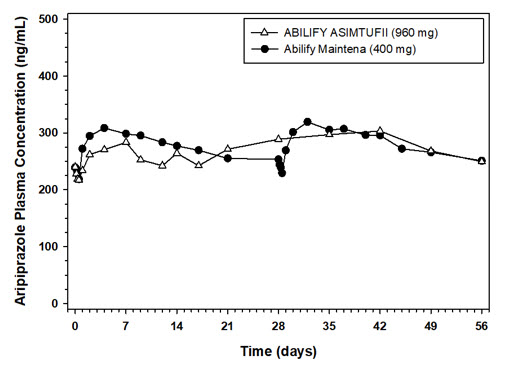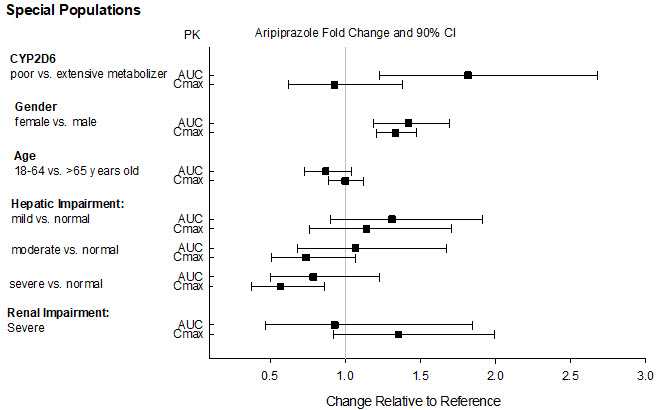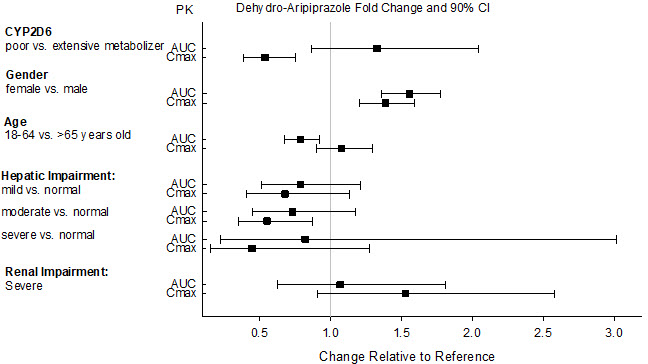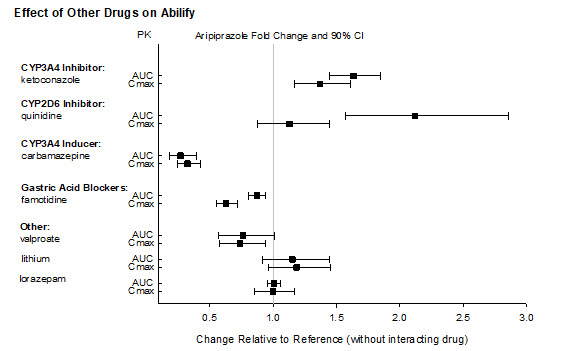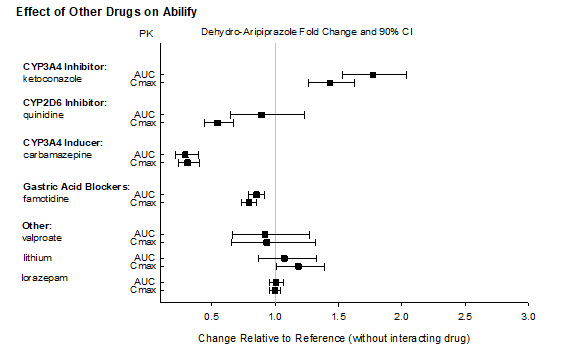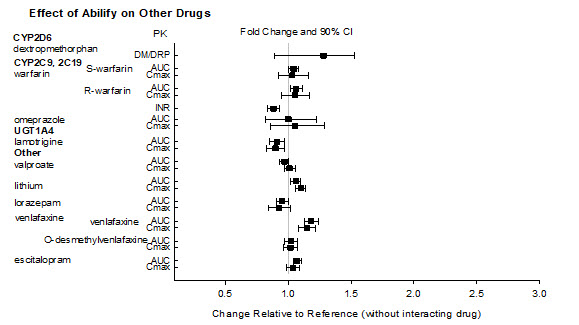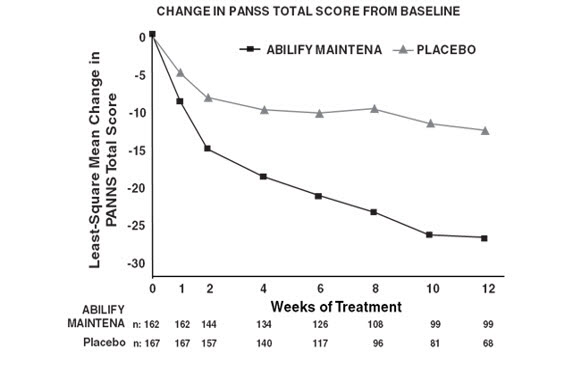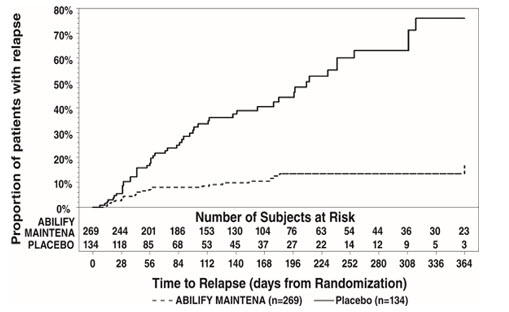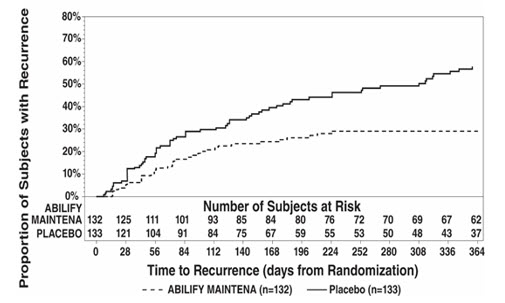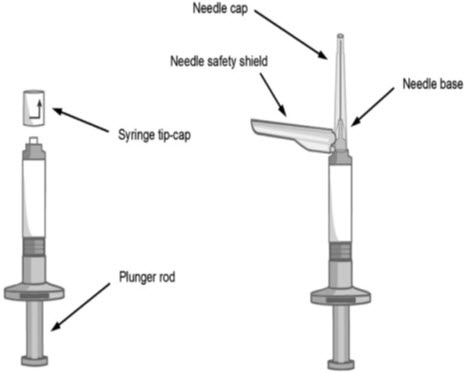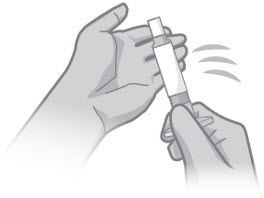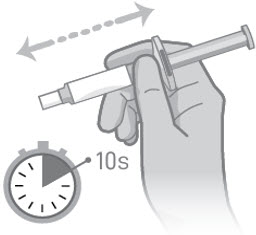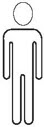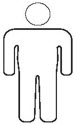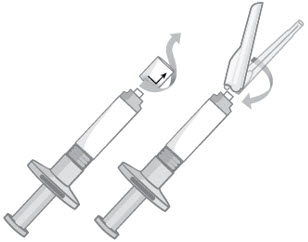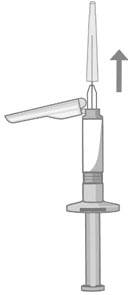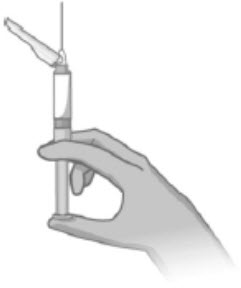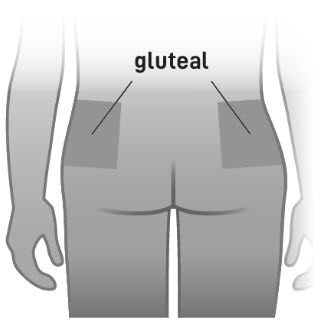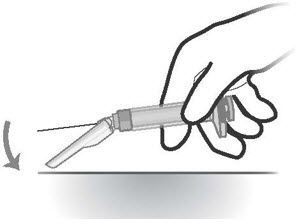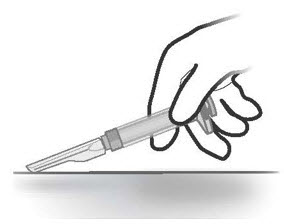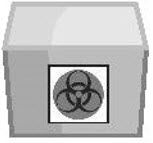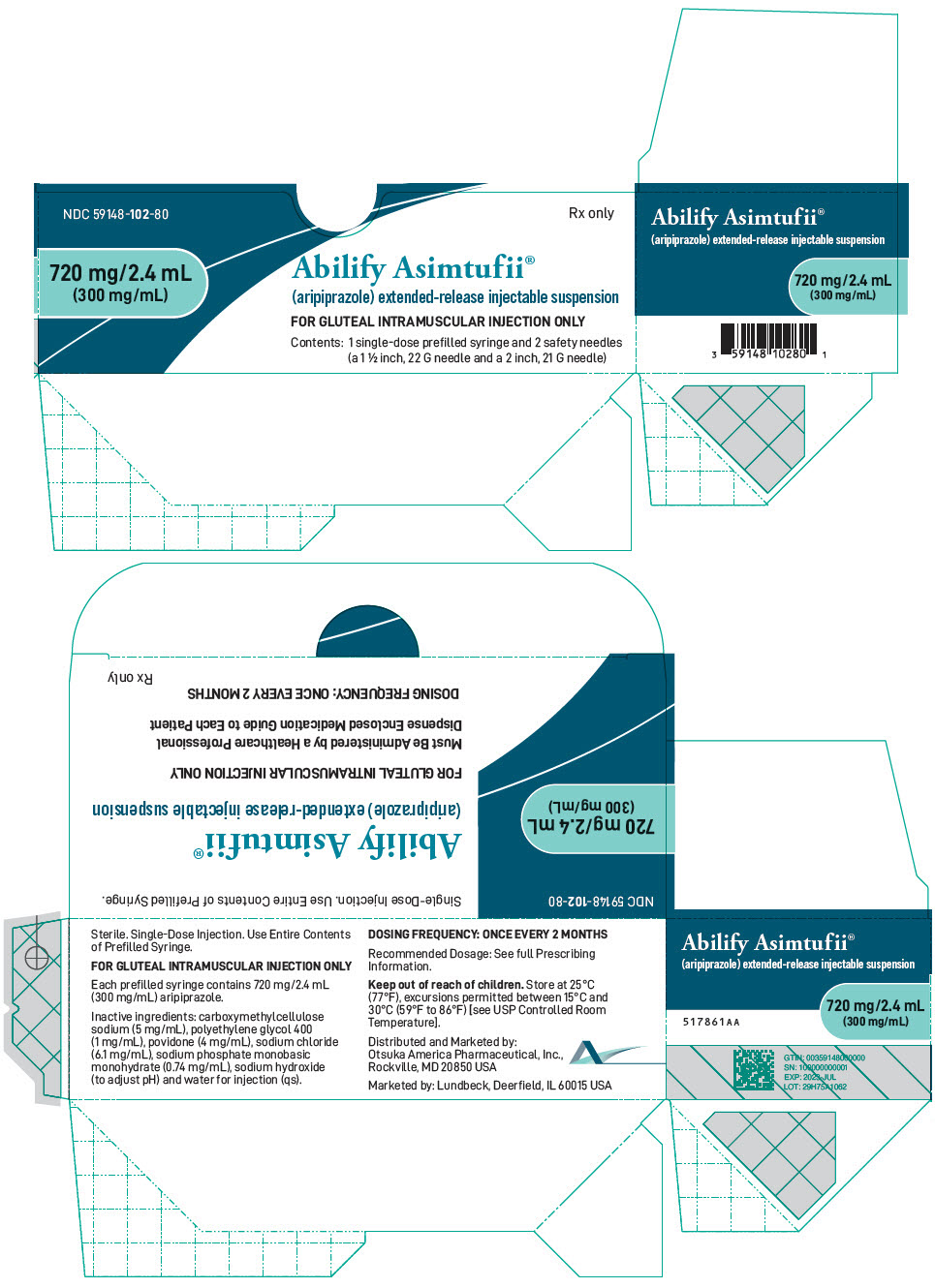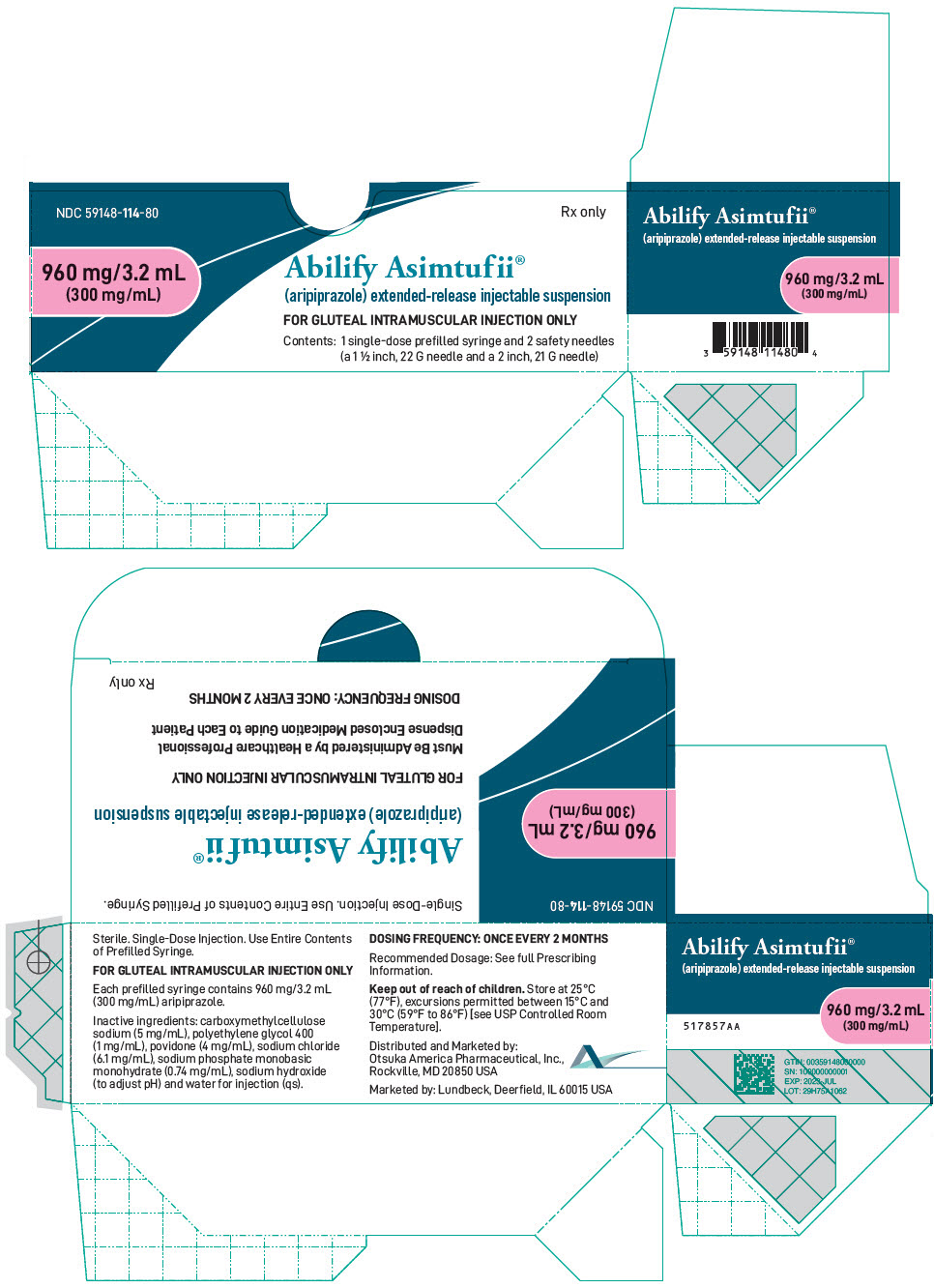 DRUG LABEL: Abilify Asimtufii
NDC: 59148-102 | Form: INJECTION, SUSPENSION, EXTENDED RELEASE
Manufacturer: Otsuka America Pharmaceutical, Inc
Category: prescription | Type: HUMAN PRESCRIPTION DRUG LABEL
Date: 20250404

ACTIVE INGREDIENTS: Aripiprazole 720 mg/2.4 mL
INACTIVE INGREDIENTS: CARBOXYMETHYLCELLULOSE SODIUM, UNSPECIFIED; POLYETHYLENE GLYCOL 400; POVIDONE, UNSPECIFIED; SODIUM CHLORIDE; SODIUM PHOSPHATE, MONOBASIC, MONOHYDRATE; SODIUM HYDROXIDE; Water

HIGHLIGHTS OF PRESCRIBING INFORMATION

These highlights do not include all the information needed to use ABILIFY ASIMTUFII safely and effectively. See full prescribing information for ABILIFY ASIMTUFII.
ABILIFY ASIMTUFII® (aripiprazole) extended-release injectable suspension, for intramuscular use
Initial U.S. Approval: 2002

WARNING: INCREASED MORTALITY IN ELDERLY PATIENTS WITH DEMENTIA-RELATED PSYCHOSIS

See full prescribing information for complete boxed warning.

- Elderly patients with dementia-related psychosis treated with antipsychotic drugs are at an increased risk of death (5.1)
- ABILIFY ASIMTUFII is not approved for the treatment of patients with dementia-related psychosis (5.1)

RECENT MAJOR CHANGES

Dosage and Administration (2.1, 2.2, 2.3, 2.4) | 3/2025

1 INDICATIONS AND USAGE

ABILIFY ASIMTUFII is an atypical antipsychotic indicated:

- for the treatment of schizophrenia in adults (1)
- as maintenance monotherapy treatment of bipolar I disorder in adults (1)

2 DOSAGE AND ADMINISTRATION

- For patients naïve to aripiprazole, establish tolerability with oral aripiprazole prior to initiating treatment with ABILIFY ASIMTUFII (2.1)
- Administer by intramuscular injection in the gluteal muscle by a healthcare professional. Do not administer by any other route (2.1)
- Recommended dosage is 960 mg administered once every 2 months as a single injection. Dose can be reduced to 720 mg in patients with adverse reactions (2.2)
- For patients currently receiving an oral antipsychotic, there are two ways to initiate treatment with ABILIFY ASIMTUFII
  - 1-day initiation: Administer one injection of ABILIFY ASIMTUFII 960 mg, one injection of Abilify Maintena 400 mg and a single oral dose of aripiprazole 20 mg (2.2)
  - 14-day initiation: In conjunction with first ABILIFY ASIMTUFII 960 mg dose, take 14 consecutive days of concurrent oral aripiprazole (10 mg to 20 mg) or current oral antipsychotic (2.2)
- For patients currently receiving Abilify Maintena
  - Administer ABILIFY ASIMTUFII 960 mg in place of the next scheduled injection of the Abilify Maintena.
- Missed doses: Dosage adjustment may be required (2.3)
- Known CYP2D6 poor metabolizers: Recommended dosage is 720 mg administered once every 2 months as a single injection (2.4)
- See Full Prescribing Information for important preparation and administration information (2.5)

3 DOSAGE FORMS AND STRENGTHS

Extended-release injectable suspension: 960 mg/3.2 mL and 720 mg/2.4 mL single-dose pre-filled syringes (3)

4 CONTRAINDICATIONS

Known hypersensitivity to aripiprazole, or to any excipients of ABILIFY ASIMTUFII (4)

5 WARNINGS AND PRECAUTIONS

- Cerebrovascular Adverse Reactions in Elderly Patients with Dementia-Related Psychosis: Increased incidence of cerebrovascular adverse reactions (e.g., stroke, transient ischemic attack, including fatalities) (5.2)
- Neuroleptic Malignant Syndrome: Manage with immediate discontinuation and close monitoring (5.3)
- Tardive Dyskinesia: Discontinue if clinically appropriate (5.4)
- Metabolic Changes: Monitor for hyperglycemia/diabetes mellitus, dyslipidemia, and weight gain (5.5)
- Pathological Gambling and Other Compulsive Behaviors: Consider dose reduction or discontinuation (5.6)
- Orthostatic Hypotension and Syncope: Monitor heart rate and blood pressure and caution in patients with known cardiovascular or cerebrovascular disease, and risk of dehydration or syncope (5.7)
- Leukopenia, Neutropenia, and Agranulocytosis: Perform complete blood counts (CBC) in patients with history of clinically significant low white blood cell count (WBC) or a history of leukopenia or neutropenia. Consider discontinuing ABILIFY ASIMTUFII if clinically significant decline in WBC in the absence of other causative factors (5.9)
- Seizures: Use cautiously in patients with a history of seizures or with conditions that lower the seizure threshold (5.10)
- Potential for Cognitive and Motor Impairment: Use caution when operating machinery (5.11)

6 ADVERSE REACTIONS

Most commonly observed adverse reactions (incidence ≥5% and at least twice the rate of placebo) were increased weight, akathisia, injection site pain, and sedation (6.1)

To report SUSPECTED ADVERSE REACTIONS, contact Otsuka America Pharmaceutical, Inc. at 1-800-438-9927 or FDA at 1-800-FDA-1088 or www.fda.gov/medwatch.

7 DRUG INTERACTIONS

Dosage adjustments for patients taking CYP2D6 inhibitors, CYP3A4 inhibitors, or CYP3A4 inducers for greater than 14 days (2.4, 7.1):

Factors | Dosage Recommendation
CYP2D6 Poor Metabolizers taking concomitant CYP3A4 inhibitors | Avoid use
Patients taking strong CYP2D6 or CYP3A4 inhibitors | 720 mg [For the 1-day initiation regimen, administer a single 20 mg oral aripiprazole, 300 mg Abilify Maintena and 720 mg ABILIFY ASIMTUFII on Day 1.]
Patients taking CYP2D6 and CYP3A4 inhibitors | Avoid use
Patients taking CYP3A4 inducers | Avoid use

8 USE IN SPECIFIC POPULATIONS

Pregnancy: May cause extrapyramidal and/or withdrawal symptoms in neonates with third trimester exposure (8.1)

Lactation: Monitor the breastfed infant for dehydration and lack of appropriate weight gain (8.2)

FULL PRESCRIBING INFORMATION

WARNING: INCREASED MORTALITY IN ELDERLY PATIENTS WITH DEMENTIA-RELATED PSYCHOSIS

Elderly patients with dementia-related psychosis treated with antipsychotic drugs are at an increased risk of death. ABILIFY ASIMTUFII is not approved for the treatment of patients with dementia-related psychosis [see Warnings and Precautions (5.1)].

1 INDICATIONS AND USAGE

ABILIFY ASIMTUFII is indicated:

- for the treatment of schizophrenia in adults
- for maintenance monotherapy treatment of bipolar I disorder in adults

2 DOSAGE AND ADMINISTRATION

2.1 Important Administration Information

For patients who have never taken aripiprazole, establish tolerability with oral aripiprazole prior to initiating treatment with ABILIFY ASIMTUFII. Due to the half-life of oral aripiprazole (i.e., 75 hours and 94 hours for aripiprazole and dehydro-aripiprazole, respectively), it may take up to 2 weeks to fully assess tolerability.

ABILIFY ASIMTUFII must be administered as an intramuscular gluteal injection by a healthcare professional. Do not administer by any other route.

For detailed preparation and administration instructions, [see Dosage and Administration (2.5)].

2.2 Recommended Dosage for ABILIFY ASIMTUFII

The recommended dosage of ABILIFY ASIMTUFII is 960 mg, administered once every 2 months (56 days after previous injection).

Patients Receiving Oral Antipsychotics

There are two ways to initiate treatment with ABILIFY ASIMTUFII in patients receiving oral antipsychotics:

1-day initiation:

- Administer one intramuscular injection of ABILIFY ASIMTUFII 960 mg in the gluteal muscle, one injection of Abilify Maintena 400 mg in a separate gluteal or deltoid muscle, and one dose of oral aripiprazole 20 mg, on the first day of treatment with ABILIFY ASIMTUFII.
- Do not administer both injections into the same muscle.

14-day initiation:

- Administer one intramuscular injection of ABILIFY ASIMTUFII 960 mg in the gluteal muscle and continue treatment with oral aripiprazole (10 mg to 20 mg) for 14 consecutive days.
- For patients already stable on another oral antipsychotic (and known to tolerate aripiprazole), administer one intramuscular injection of ABILIFY ASIMTUFII 960 mg in the gluteal muscle and continue treatment with the oral antipsychotic for 14 consecutive days.

Patients Receiving Abilify Maintena

For patients receiving Abilify Maintena 400 mg (once monthly dosing), administer ABILIFY ASIMTUFII 960 mg (once every 2 month dosing) in place of the next scheduled injection of the Abilify Maintena. The first ABILIFY ASIMTUFII injection may be administered in place of the second, or later injection of Abilify Maintena.

If there are adverse reactions with the ABILIFY ASIMTUFII 960 mg dosage, the dosage may be reduced to 720 mg once every 2 months.

Patients may be given the ABILIFY ASIMTUFII injection up to 2 weeks before or 2 weeks after the 2-month scheduled timepoint.

2.3 Missed Doses

If more than 8 weeks and less than 14 weeks have elapsed since the last injection, administer the next dose of ABILIFY ASIMTUFII as soon as possible. The once every 2 month schedule should be resumed.

If more than 14 weeks have elapsed since the last injection, restart treatment with either 1-day initiation or 14-day initiation with ABILIFY ASIMTUFII [see Dosage and Administration (2.2)].

2.4 Dosage Modifications for Cytochrome P450 Considerations

Dosage adjustments for patients who are CYP2D6 poor metabolizers and/or in patients taking concomitant strong CYP3A4 inhibitors or CYP2D6 inhibitors for more than 14 days are described in Table 1.

If the CYP3A4 inhibitor or CYP2D6 inhibitor is withdrawn, the dosage of ABILIFY ASIMTUFII may need to be increased to the previous dose.

Dosage adjustments are not recommended for patients with concomitant use of CYP3A4 inhibitors, CYP2D6 inhibitors or CYP3A4 inducers for less than 14 days.

Table 1: Dosage Recommendations for ABILIFY ASIMTUFII in Patients Who are Known CYP2D6 Poor Metabolizers, Patients Taking Concomitant CYP2D6 Inhibitors, 3A4 Inhibitors, or CYP3A4 Inducers for Greater than 14 days
Factors | Dosage Recommendation
CYP2D6 Poor Metabolizers
Known CYP2D6 Poor Metabolizers | 720 mg once every 2 months [For the 1-day initiation regimen, administer a single 20 mg oral aripiprazole, 300 mg Abilify Maintena and 720 mg ABILIFY ASIMTUFII on Day 1.]
Known CYP2D6 Poor Metabolizers taking concomitant CYP3A4 inhibitors | Avoid use
Patients Taking 960 mg of ABILIFY ASIMTUFII
Concomitant use of ABILIFY ASIMTUFII with Strong CYP2D6 inhibitors | 720 mg once every 2 months
Concomitant use of ABILIFY ASIMTUFII with Strong CYP3A4 inhibitors | 720 mg once every 2 months
Concomitant use of ABILIFY ASIMTUFII with Strong CYP2D6 and Strong CYP3A4 inhibitors | Avoid use
Concomitant use of ABILIFY ASIMTUFII with CYP3A4 inducers | Avoid use

2.5 Preparation and Administration Instructions

- Read the complete instructions for preparation and administration below and consider referring to the separate Healthcare Provider "Instructions for Use" for additional preparation and administration considerations.
- To be prepared and administered by a healthcare professional only.
- For gluteal intramuscular injection only. Do not administer by any other route.
- Prior to administration, visually inspect ABILIFY ASIMTUFII pre-filled syringe for particulate matter and discoloration. The suspension should appear to be a uniform, homogeneous suspension that is opaque and milky-white in color. Do not use ABILIFY ASIMTUFII pre-filled syringe if the suspension is discolored, or particulate matter is present
  - Each kit contains one sterile pre-filled syringe containing ABILIFY ASIMTUFII 720 mg or 960 mg and two safety needles:
    - One sterile 1 ½ inch, 22 gauge needle (in black packaging)
    - One sterile 2 inch, 21 gauge needle (in green packaging)

Preparation Prior to Administration

- Remove the ABILIFY ASIMTUFII pre-filled syringe from the package.
- Tap the syringe on your hand at least 10 (ten) times (Figure 1).
- After tapping, shake the syringe vigorously for at least 10 (ten) seconds, until the medication is uniform (Figure 2).
  Figure 1
  Figure 2

Select the appropriate needle

Needle selection is determined by patient body type.

For gluteal intramuscular administration only.

- For non-obese patients - 22-gauge, 1.5-inch (38 mm) safety needle with needle protection device (needle in black packaging)
- For obese patients - 21-gauge, 2-inch (51 mm) safety needle with needle protection device (needle in green packaging)

Attach the needle

- Twist and pull off the pre-filled syringe tip-cap (Figure 3).
- While holding the base of the needle, ensure the needle is firmly seated on the safety device with a push. Gently twist clockwise until SECURELY fitted (Figure 3).
  Figure 3

Expel Air

- When you are ready to administer the injection of ABILIFY ASIMTUFII, hold the pre-filled syringe upright and remove the needle-cap straight up (Figure 4). Do not twist the needle-cap, as this may loosen the needle from the syringe.
  Figure 4
- Slowly advance the plunger rod upward to expel the air and until the suspension fills needle base (Figure 5).
  Figure 5

Inject the dose

- Slowly inject the entire contents of the pre-filled syringe intramuscularly into the gluteal muscle of the patient (Figure 6).

Do not administer by any other route.

Do not massage the injection site.

Figure 6

Disposal Procedure

- After the injection, press the safety shield on a hard surface to cover and lock shield over the needle (Figures 7 and 8)
  Figure 7
  Figure 8
- Immediately discard used syringe and the unused needle in an approved sharps container.
- The unused needle should not be saved for future use.

3 DOSAGE FORMS AND STRENGTHS

Extended-release injectable suspension: sterile, white to off-white, aqueous suspension in a single-dose, pre-filled syringe.

Table 2: ABILIFY ASIMTUFII Presentations
Dose Strength | Volume | Label Color | Syringe Tip Wrap
720 mg | 2.4 mL | Light Blue | Aqua
960 mg | 3.2 mL | Pink | Light Blue

4 CONTRAINDICATIONS

ABILIFY ASIMTUFII is contraindicated in patients with a known hypersensitivity to aripiprazole, or any of the excipients. Hypersensitivity reactions ranging from pruritus/urticaria to anaphylaxis have been reported in patients receiving aripiprazole [see Adverse Reactions (6.1)].

5 WARNINGS AND PRECAUTIONS

5.1 Increased Mortality in Elderly Patients with Dementia-Related Psychosis

Elderly patients with dementia-related psychosis treated with antipsychotic drugs are at an increased risk of death. Analyses of 17 placebo-controlled trials (modal duration of 10 weeks), largely in patients taking atypical antipsychotic drugs, revealed a risk of death in drug-treated patients of between 1.6 to 1.7 times the risk of death in placebo-treated patients. Over the course of a typical 10-week controlled trial, the rate of death in drug-treated patients was about 4.5%, compared to a rate of about 2.6% in the placebo group.

Although the causes of death were varied, most of the deaths appeared to be either cardiovascular (e.g., heart failure, sudden death) or infectious (e.g., pneumonia) in nature. Observational studies suggest that, similar to atypical antipsychotic drugs, treatment with conventional antipsychotic drugs may increase mortality. The extent to which the findings of increased mortality in observational studies may be attributed to the antipsychotic drug as opposed to some characteristic(s) of the patients is not clear.

ABILIFY ASIMTUFII is not approved for the treatment of patients with dementia-related psychosis [see Boxed Warning and Warnings and Precautions (5.2)].

5.2 Cerebrovascular Adverse Reactions, Including Stroke in Elderly Patients with Dementia-Related Psychosis

In placebo-controlled clinical studies (two flexible-dose and one fixed-dose study) of dementia-related psychosis, there was an increased incidence of cerebrovascular adverse reactions (e.g., stroke, transient ischemic attack), including fatalities, in oral aripiprazole-treated patients (mean age: 84 years; range: 78 to 88 years). In the fixed-dose study, there was a statistically significant dose response relationship for cerebrovascular adverse reactions in patients treated with oral aripiprazole. ABILIFY ASIMTUFII is not approved for the treatment of patients with dementia-related psychosis [see Warnings and Precautions (5.1)].

5.3 Neuroleptic Malignant Syndrome

Neuroleptic Malignant Syndrome (NMS), a potentially fatal symptom complex has been reported with antipsychotic drugs, including aripiprazole. Rare cases of NMS have been reported during aripiprazole treatment in the global clinical database.

Clinical manifestations of NMS are hyperpyrexia, muscle rigidity, altered mental status, and evidence of autonomic instability (irregular pulse or blood pressure, tachycardia, diaphoresis, and cardiac dysrhythmia). Additional signs may include elevated creatine phosphokinase, myoglobinuria (rhabdomyolysis) and acute renal failure.

If NMS is suspected, immediately discontinue ABILIFY ASIMTUFII and provide symptomatic treatment and monitoring.

5.4 Tardive Dyskinesia

Tardive dyskinesia, a syndrome of potentially irreversible, involuntary, dyskinetic movements may develop in patients treated with antipsychotic drugs. Although the prevalence of the syndrome appears to be highest among the elderly, especially elderly women, it is impossible to predict which patients will develop the syndrome. Whether antipsychotic drug products differ in their potential to cause tardive dyskinesia is unknown.

The risk of developing tardive dyskinesia and the likelihood that it will become irreversible appear to increase as the duration of treatment and the total cumulative dose increases. The syndrome can develop, after relatively brief treatment periods at low doses. It may also occur after discontinuation of treatment.

Tardive dyskinesia may remit, partially or completely, if antipsychotic treatment is discontinued. Antipsychotic treatment itself may suppress (or partially suppress) the signs and symptoms of the syndrome and may mask the underlying process. The effect of symptomatic suppression on the long-term course of the syndrome is unknown.

Given these considerations, ABILIFY ASIMTUFII should be prescribed in a manner that is most likely to minimize the occurrence of tardive dyskinesia. Chronic antipsychotic treatment should generally be reserved for patients who suffer from a chronic illness that 1) is known to respond to antipsychotic drugs and 2) for whom alternative, equally effective, but potentially less harmful treatments are not available or appropriate. In patients who do require chronic treatment, the smallest dose and the shortest duration of treatment producing a satisfactory clinical response should be sought. The need for continued treatment should be reassessed periodically.

If signs and symptoms of tardive dyskinesia appear in a patient treated with ABILIFY ASIMTUFII, drug discontinuation should be considered. However, some patients may require treatment with ABILIFY ASIMTUFII despite the presence of the syndrome.

5.5 Metabolic Changes

Atypical antipsychotic drugs have been associated with metabolic changes including hyperglycemia/diabetes mellitus, dyslipidemia, and body weight gain. While all drugs in the class have been shown to produce some metabolic changes, each drug has its own specific risk profile.

Hyperglycemia/Diabetes Mellitus

Hyperglycemia, in some cases extreme and associated with diabetic ketoacidosis, hyperosmolar coma, or death, have been reported in patients treated with atypical antipsychotics. There have been reports of hyperglycemia in patients treated with aripiprazole [see Adverse Reactions (6.1)]. Assessment of the relationship between atypical antipsychotic use and glucose abnormalities is complicated by the possibility of an increased background risk of diabetes mellitus in patients with schizophrenia and the increasing incidence of diabetes mellitus in the general population. Given these confounders, the relationship between atypical antipsychotic use and hyperglycemia-related adverse reactions is not completely understood. However, epidemiological studies suggest an increased risk of hyperglycemia-related adverse reactions in patients treated with the atypical antipsychotics.

Patients with an established diagnosis of diabetes mellitus who are started on atypical antipsychotics, including ABILIFY ASIMTUFII, should be monitored regularly for worsening of glucose control. Patients with risk factors for diabetes mellitus (e.g., obesity, family history of diabetes), who are starting treatment with atypical antipsychotics should undergo fasting blood glucose testing at the beginning of treatment and periodically during treatment. Any patient treated with atypical antipsychotics, including ABILIFY ASIMTUFII, should be monitored for symptoms of hyperglycemia including polydipsia, polyuria, polyphagia, and weakness. Patients who develop symptoms of hyperglycemia during treatment with atypical antipsychotics, including ABILIFY ASIMTUFII, should undergo fasting blood glucose testing. In some cases, hyperglycemia has resolved when the atypical antipsychotic was discontinued; however, some patients required continuation of anti-diabetic treatment despite discontinuation of the atypical antipsychotic drug.

In a short-term, placebo-controlled randomized trial in adults with schizophrenia, the mean change in fasting glucose was +9.8 mg/dL (N=88) in the Abilify Maintena-treated patients (once monthly dosing) and +0.7 mg/dL (N=59) in the placebo-treated patients. Table 3 shows the proportion of Abilify Maintena-treated patients with normal and borderline fasting glucose at baseline and their changes in fasting glucose measurements.

Table 3: Proportion of Patients with Potential Clinically Relevant Changes in Fasting Glucose from a 12-Week Placebo-Controlled Monotherapy Trial with Abilify Maintena in Adult Patients with Schizophrenia
 | Category Change (at least once) from Baseline | Treatment Arm | n/N [N = the total number of subjects who had a measurement at baseline and at least one post-baseline result. n = the number of subjects with a potentially clinically relevant shift.] | %
Fasting Glucose | Normal to High (<100 mg/dL to ≥126 mg/dL) | Abilify Maintena | 7/88 | 8.0
Fasting Glucose | Normal to High (<100 mg/dL to ≥126 mg/dL) | Placebo | 0/75 | 0.0
Fasting Glucose | Borderline to High (≥100 mg/dL and <126 mg/dL to ≥126 mg/dL) | Abilify Maintena | 1/33 | 3.0
Fasting Glucose | Borderline to High (≥100 mg/dL and <126 mg/dL to ≥126 mg/dL) | Placebo | 3/33 | 9.1

During a 52-week, open-label bipolar I disorder study in those patients who initiated Abilify Maintena treatment, 1.1% with normal baseline fasting glucose experienced a shift to high while receiving Abilify Maintena and 9.8% with borderline fasting glucose experienced a shift to high. Combined, 2.9% of these patients with normal or borderline fasting glucose experienced shifts to high fasting glucose during this trial.

Dyslipidemia

Undesirable alterations in lipids have been observed in patients treated with atypical antipsychotics.

Table 4 shows the proportion of adult patients from one short-term, placebo-controlled randomized trial in adults with schizophrenia taking Abilify Maintena (once monthly dosing), with changes in total cholesterol, fasting triglycerides, fasting LDL cholesterol and HDL cholesterol.

Table 4: Proportion of Patients with Potential Clinically Relevant Changes in Blood Lipid Parameters From a 12-Week Placebo-Controlled Monotherapy Trial with Abilify Maintena in Adults with Schizophrenia
 | Treatment Arm | n/N [N = the total number of subjects who had a measurement at baseline and at least one post-baseline result. n = the number of subjects with a potentially clinically relevant shift.] | %
Total Cholesterol Normal to High (<200 mg/dL to ≥240 mg/dL) | Abilify Maintena | 3/83 | 3.6
Total Cholesterol Normal to High (<200 mg/dL to ≥240 mg/dL) | Placebo | 2/73 | 2.7
Borderline to High (200~<240 mg/dL to ≥240 mg/dL) | Abilify Maintena | 6/27 | 22.2
Borderline to High (200~<240 mg/dL to ≥240 mg/dL) | Placebo | 2/19 | 10.5
Any increase (≥40 mg/dL) | Abilify Maintena | 15/122 | 12.3
Any increase (≥40 mg/dL) | Placebo | 6/110 | 5.5
Fasting Triglycerides Normal to High (<150 mg/dL to ≥200 mg/dL) | Abilify Maintena | 7/98 | 7.1
Fasting Triglycerides Normal to High (<150 mg/dL to ≥200 mg/dL) | Placebo | 4/78 | 5.1
Borderline to High (150~<200 mg/dL to ≥200 mg/dL) | Abilify Maintena | 3/11 | 27.3
Borderline to High (150~<200 mg/dL to ≥200 mg/dL) | Placebo | 4/15 | 26.7
Any increase (≥50 mg/dL) | Abilify Maintena | 24/122 | 19.7
Any increase (≥50 mg/dL) | Placebo | 20/110 | 18.2
Fasting LDL Cholesterol Normal to High (<100 mg/dL to ≥160 mg/dL) | Abilify Maintena | 1/59 | 1.7
Fasting LDL Cholesterol Normal to High (<100 mg/dL to ≥160 mg/dL) | Placebo | 1/51 | 2.0
Borderline to High (100~<160 mg/dL to ≥160 mg/dL) | Abilify Maintena | 5/52 | 9.6
Borderline to High (100~<160 mg/dL to ≥160 mg/dL) | Placebo | 1/41 | 2.4
Any increase (≥30 mg/dL) | Abilify Maintena | 17/120 | 14.2
Any increase (≥30 mg/dL) | Placebo | 9/103 | 8.7
HDL Cholesterol Normal to Low (≥40 mg/dL to <40 mg/dL) | Abilify Maintena | 14/104 | 13.5
HDL Cholesterol Normal to Low (≥40 mg/dL to <40 mg/dL) | Placebo | 11/87 | 12.6
Any decrease (≥20 mg/dL) | Abilify Maintena | 7/122 | 5.7
 | Placebo | 12/110 | 10.9

During a 52-week, open-label bipolar I disorder study in those patients who initiated Abilify Maintena, shifts from baseline in fasting cholesterol from normal to high were reported in 2.1% (total cholesterol) and 2.2% (LDL cholesterol) and shifts from baseline from normal to low were reported in 8.5% (HDL cholesterol). Of these patients with normal baseline triglycerides, 3.6% experienced shifts to high, and 0.0% experienced shifts to very high. Combined, 1.0% of these patients with normal or borderline fasting triglycerides experienced shifts to very high fasting triglycerides during this trial.

Weight Gain

Weight gain has been observed with atypical antipsychotic use. Clinical monitoring of weight is recommended.

In one short-term, placebo-controlled trial in adult patients with schizophrenia with Abilify Maintena (once monthly dosing), the mean change in body weight at Week 12 was +3.5 kg (N=99) in the Abilify Maintena-treated patients and +0.8 kg (N=66) in the placebo-treated patients.

Table 5 shows the percentage of adult patients with schizophrenia with weight gain ≥7% of body weight in a short-term, placebo-controlled trial with Abilify Maintena.

Table 5: Percentage of Patients From a 12-Week Placebo-Controlled Trial with Abilify Maintena in Adult Patients with Schizophrenia with Weight Gain ≥7% of Body Weight
 | Treatment Arm | N [N = the total number of subjects who had a measurement at baseline and at least one post-baseline result.] | Patients n (%)
Weight gain ≥7% of body weight | Abilify Maintena | 144 | 31 (21.5)
Weight gain ≥7% of body weight | Placebo | 141 | 12 (8.5)

During a 52-week, open-label bipolar I disorder study in those patients who initiated Abilify Maintena, 1.8% discontinued Abilify Maintena treatment due to weight increase. Abilify Maintena was associated with mean increase from baseline in weight of 1.0 kg at Week 52. In this trial, 21.4% of these patients demonstrated ≥7% increase in body weight and 15.4% demonstrated a ≥7% decrease in body weight.

5.6 Pathological Gambling and Other Compulsive Behaviors

Post-marketing case reports suggest that patients can experience intense urges, particularly for gambling, and the inability to control these urges while taking aripiprazole. Other compulsive urges, reported less frequently, include: sexual urges, shopping, eating or binge eating, and other impulsive or compulsive behaviors. Because patients may not recognize these behaviors as abnormal, it is important for prescribers to ask patients or their caregivers specifically about the development of new or intense gambling urges, compulsive sexual urges, compulsive shopping, binge or compulsive eating, or other urges while being treated with aripiprazole. It should be noted that impulse-control symptoms can be associated with the underlying disorder. In some cases, although not all, urges were reported to have stopped when the dose was reduced, or the medication was discontinued. Compulsive behaviors may result in harm to the patient and others if not recognized. Consider dose reduction or stopping the medication if a patient develops such urges.

5.7 Orthostatic Hypotension and Syncope

ABILIFY ASIMTUFII may cause orthostatic hypotension, perhaps due to its α1-adrenergic receptor antagonism. Associated reactions related to orthostatic hypotension can include dizziness, tachycardia, and in some patients, syncope. In the short-term, placebo-controlled trial in adults with schizophrenia, the adverse reaction of presyncope was reported in 1/167 (0.6%) of patients treated with Abilify Maintena (once monthly dosing), while syncope and orthostatic hypotension were each reported in 1/172 (0.6%) of patients treated with placebo. During the stabilization phase of the randomized-withdrawal (maintenance) study in adult patients with schizophrenia, orthostasis-related adverse events were reported in 4/576 (0.7%) of patients treated with Abilify Maintena, including abnormal orthostatic blood pressure (1/576, 0.2%), postural dizziness (1/576, 0.2%), presyncope (1/576, 0.2%) and orthostatic hypotension (1/576, 0.2%).

In the short-term placebo-controlled trial of Abilify Maintena in adults with schizophrenia, there were no patients in either treatment group with a significant orthostatic change in blood pressure (defined as a decrease in systolic blood pressure ≥20 mmHg accompanied by an increase in heart rate ≥25 bpm when comparing standing to supine values). During the stabilization phase of the randomized-withdrawal (maintenance) study in adult patients with schizophrenia, the incidence of significant orthostatic change in blood pressure was 0.2% (1/575).

Use ABILIFY ASIMTUFII with caution in patients with known cardiovascular disease (heart failure, history of myocardial infarction or ischemia, conduction abnormalities), cerebrovascular disease, or conditions that predispose the patient to hypotension (e.g., dehydration, hypovolemia, and treatment with antihypertensive medications). Monitoring of orthostatic vital signs should be considered in patients who are vulnerable to hypotension.

5.8 Falls

Antipsychotics, including ABILIFY ASIMTUFII, may cause somnolence, postural hypotension, motor and sensory instability which may lead to falls and, consequently, fractures or other fall-related injuries. For patients with diseases, conditions, or medications that could exacerbate these effects, complete fall risk assessments when initiating antipsychotic treatment and recurrently for patients on long-term antipsychotic therapy.

5.9 Leukopenia, Neutropenia, and Agranulocytosis

In clinical trials and post-marketing experience, leukopenia and neutropenia have been reported temporally related to antipsychotic agents, including aripiprazole. Agranulocytosis has also been reported [see Adverse Reactions (6.1)].

Possible risk factors for leukopenia/neutropenia include pre-existing low white blood cell count (WBC) absolute neutrophil count (ANC) and a history of drug-induced leukopenia/neutropenia. In patients with a history of a clinically significant low WBC/ANC or drug-induced leukopenia/neutropenia, perform a complete blood count (CBC) frequently during the first few months of therapy. In such patients, consider discontinuation of ABILIFY ASIMTUFII at the first sign of a clinically significant decline in WBC in the absence of other causative factors.

Monitor patients with clinically significant neutropenia for fever or other symptoms or signs of infection and treat promptly if such symptoms or signs occur. Discontinue ABILIFY ASIMTUFII in patients with severe neutropenia (ANC<1000/mm^3) and follow their WBC counts until recovery.

5.10 Seizures

As with other antipsychotic drugs, use ABILIFY ASIMTUFII cautiously in patients with a history of seizures or other conditions that potentially lower the seizure threshold. Conditions that lower the seizure threshold may be more prevalent in a population of 65 years or older.

5.11 Potential for Cognitive and Motor Impairment

ABILIFY ASIMTUFII, like other antipsychotics, may impair judgment, thinking, or motor skills. Instruct patients to be cautious about performing activities that require mental alertness such as operating hazardous machinery or operating a motor vehicle, until they are reasonably certain that therapy with ABILIFY ASIMTUFII does not affect them adversely.

5.12 Body Temperature Regulation

Disruption of the body's ability to reduce core body temperature has been attributed to antipsychotic agents. Appropriate care is advised when prescribing ABILIFY ASIMTUFII for patients who will be experiencing conditions which may contribute to an elevation in core body temperature, (e.g., exercising strenuously, exposure to extreme heat, receiving concomitant medication with anticholinergic activity, or being subject to dehydration).

5.13 Dysphagia

Esophageal dysmotility and aspiration have been associated with antipsychotic drug use, including aripiprazole. ABILIFY ASIMTUFII and other antipsychotic drugs should be used cautiously in patients at risk for aspiration.

6 ADVERSE REACTIONS

The following adverse reactions are discussed in more detail in other sections of the labeling:

- Increased Mortality in Elderly Patients with Dementia - Related Psychosis Use [see Boxed Warning and Warnings and Precautions (5.1)]
- Cerebrovascular Adverse Reactions, Including Stroke in Elderly Patients with Dementia-Related Psychosis [see Warnings and Precautions (5.2)]
- Neuroleptic Malignant Syndrome [see Warnings and Precautions (5.3)]
- Tardive Dyskinesia [see Warnings and Precautions (5.4)]
- Metabolic Changes [see Warnings and Precautions (5.5)]
- Pathological Gambling and Other Compulsive Behaviors [see Warnings and Precautions (5.6)]
- Orthostatic Hypotension and Syncope [see Warnings and Precautions (5.7)]
- Falls [see Warnings and Precautions (5.8)]
- Leukopenia, Neutropenia, and Agranulocytosis [see Warnings and Precautions (5.9)]
- Seizures [see Warnings and Precautions (5.10)]
- Potential for Cognitive and Motor Impairment [see Warnings and Precautions (5.11)]
- Body Temperature Regulation [see Warnings and Precautions (5.12)]
- Dysphagia [see Warnings and Precautions (5.13)]

6.1 Clinical Trials Experience

Because clinical trials are conducted under widely varying conditions, adverse reaction rates observed in the clinical trials of a drug cannot be directly compared to rates in the clinical trials of another drug and may not reflect the rates observed in practice.

The safety of ABILIFY ASIMTUFII for the treatment of schizophrenia in adults and maintenance monotherapy treatment of bipolar I disorder in adults is based on adequate and well-controlled studies of Abilify Maintena. The safety data from those studies is presented below.

Safety Database of Abilify Maintena (once monthly dosing) and Oral Aripiprazole.

Oral aripiprazole has been evaluated for safety in 16,114 adult patients who participated in multiple-dose, clinical trials in schizophrenia and other indications, and who had approximately 8,578 patient-years of exposure to oral aripiprazole. A total of 3,901 patients were treated with oral aripiprazole for at least 180 days, 2,259 patients were treated with oral aripiprazole for at least 360 days, and 933 patients continuing aripiprazole treatment for at least 720 days.

Abilify Maintena (once monthly dosing) has been evaluated for safety in 2,128 adult patients in clinical trials in schizophrenia, with approximately 2,633 patient-years of exposure to Abilify Maintena. A total of 1,229 patients were treated with Abilify Maintena for at least 180 days (at least 7 consecutive injections) and 935 patients treated with Abilify Maintena had at least 1 year of exposure (at least 13 consecutive injections).

Abilify Maintena has been evaluated for safety in 804 adult patients in clinical trials in bipolar I disorder, with approximately 530 patient-years of exposure to Abilify Maintena. A total of 419 patients were treated with Abilify Maintena for at least 180 days (at least 7 consecutive injections) and 287 patients treated with Abilify Maintena had at least 1 year of exposure (at least 13 consecutive injections).

Safety Database of ABILIFY ASIMTUFII (once every 2 month dosing)

In a 32 week open-label study of ABILIFY ASIMTUFII in adult patients with schizophrenia or bipolar I disorder, 266 patients were randomized to receive either ABILIFY ASIMTUFII 960 mg (132 patients) or Abilify Maintena 400 mg (134 patients). A total of the 132 patients received at least one injection of ABILIFY ASIMTUFII, a total of 114 patients received at least two consecutive injections (4 months treatment) of ABILIFY ASIMTUFII, and a total of 104 patients received at least four consecutive injections (8 months treatment) of ABILIFY ASIMTUFII. Of the total 266 patients receiving ABILIFY ASIMTUFII 960 mg or Abilify Maintena 400 mg, 185 had schizophrenia and 81 had bipolar I disorder. Injection site reactions for ABILIFY ASIMTUFII (once every 2 month dosing) presented in this section is based on this open-label study (see section titled "Injection Site Reactions with Abilify ASIMTUFII").

Adverse Reactions in Studies with Abilify Maintena (once monthly dosing)

The conditions and duration of treatment with Abilify Maintena included double-blind and open-label studies. The safety data presented below are derived from the 12-week double-blind placebo-controlled study of Abilify Maintena in adult patients with schizophrenia.

Most Commonly Observed Adverse Reactions in Double-Blind, Placebo-Controlled Clinical Trials in Schizophrenia with Abilify Maintena

Based on the placebo-controlled trial of Abilify Maintena in schizophrenia, the most commonly observed adverse reactions associated with the use of Abilify Maintena in patients (incidence of 5% or greater and aripiprazole incidence at least twice that for placebo) were increased weight (16.8% vs. 7.0%), akathisia (11.4% vs. 3.5%), injection site pain (5.4% vs. 0.6%) and sedation (5.4% vs. 1.2%).

Commonly Reported Adverse Reactions in Double-Blind, Placebo-Controlled Clinical Trials in Schizophrenia with Abilify Maintena

The following findings are based on the double-blind, placebo-controlled trial that compared Abilify Maintena 400 mg or 300 mg to placebo in patients with schizophrenia. Table 6 lists the adverse reactions reported in 2% or more of Abilify Maintena-treated patients and at a greater proportion than in the placebo group.

Table 6: Adverse Reactions in ≥2% of Adult Patients with Schizophrenia Treated with Abilify Maintena in a 12-Week Double-Blind, Placebo-Controlled Study [This table does not include adverse reactions which had an incidence equal to or less than placebo.]
Preferred Term | Abilify Maintena (n=167) | Placebo (n=172)
Gastrointestinal Disorders
Constipation | 10 | 7
Dry Mouth | 4 | 2
Diarrhea | 3 | 2
Vomiting | 3 | 1
Abdominal Discomfort | 2 | 1
General Disorders and Administration Site Conditions
Injection Site Pain | 5 | 1
Infections and Infestations
Upper Respiratory Tract Infection | 4 | 2
Investigations
Increased Weight | 17 | 7
Decreased Weight | 4 | 2
Musculoskeletal and Connective Tissue Disorders
Arthralgia | 4 | 1
Back Pain | 4 | 2
Myalgia | 4 | 2
Musculoskeletal pain | 3 | 1
Nervous System Disorders
Akathisia | 11 | 4
Sedation | 5 | 1
Dizziness | 4 | 2
Tremor | 3 | 1
Respiratory, Thoracic and Mediastinal
Nasal Congestion | 2 | 1

Demographic Differences

An examination of population subgroups was performed across demographic subgroup categories for adverse reactions experienced by at least 5% of Abilify Maintena patients at least twice the rate of placebo (i.e., increased weight, akathisia, injection site pain, and sedation) in the double-blind placebo-controlled trial. This analysis did not reveal evidence of differences in safety differential adverse reaction incidence on the basis of age, gender, or race alone; however, there were few patients ≥65 years of age.

Injection Site Reactions with ABILIFY ASIMTUFII

ABILIFY ASIMTUFII was evaluated in 266 patients with schizophrenia or bipolar I disorder in an open-label, multiple-dose, randomized, parallel-arm multi-center study.

The percentage of patients in the open-label study reporting any injection site-related adverse reactions (all reported as injection site pain) was 19% for patients treated with ABILIFY ASIMTUFII 960 mg and 9% for patients treated with Abilify Maintena 400 mg. In both treatment groups, the majority of the injection site pain events coincided with the first injection of ABILIFY ASIMTUFII 960 mg (21/24 patients) or Abilify Maintena 400 mg (7/12 patients), was reported with decreasing frequency upon subsequent injections. The overall mean visual analog scale scores (0=no pain to 100=unbearably painful) for patient reported rating of pain were similar in both treatment groups at the last injection: 0.8 pre-dose and 1.4 post-dose for the ABILIFY ASIMTUFII 960 mg group compared to 1.3 post-dose for the Abilify Maintena 400 mg group.

Extrapyramidal Symptoms (EPS)

In the short-term, placebo-controlled trial of Abilify Maintena in adults with schizophrenia, the incidence of reported EPS-related events, excluding events related to akathisia, for Abilify Maintena-treated patients was 9.6% vs. 5.2% for placebo. The incidence of akathisia-related events for Abilify Maintena-treated patients was 11.5% vs. 3.5% for placebo.

Dystonia

Symptoms of dystonia, prolonged abnormal contractions of muscle groups, may occur in susceptible individuals during the first few days of treatment. Dystonic symptoms include: spasm of the neck muscles, sometimes progressing to tightness of the throat, swallowing difficulty, difficulty breathing, and/or protrusion of the tongue. While these symptoms can occur at low doses, they occur more frequently and with greater severity with high potency and at higher doses of first-generation antipsychotic drugs. An elevated risk of acute dystonia is observed in males and younger age groups. In the short-term, placebo-controlled trial of Abilify Maintena in adults with schizophrenia, the incidence of dystonia was 1.8% for Abilify Maintena vs. 0.6% for placebo.

Neutropenia

In the short-term, placebo-controlled trial of Abilify Maintena in adults with schizophrenia, the incidence of neutropenia (absolute neutrophil count ≤1.5 thous/mcL) for Abilify Maintena-treated patients was 5.7% vs. 2.1% for placebo. An absolute neutrophil count of <1 thous/mcL (i.e., 0.95 thous/mcL) was observed in only one patient on Abilify Maintena and resolved spontaneously without any associated adverse reactions [see Warnings and Precautions (5.9)].

Other Adverse Reactions During the Clinical Trial Evaluation of Abilify Maintena

The following listing does not include reactions: 1) already listed in previous tables or elsewhere in labeling, 2) for which a drug cause was remote, 3) which were so general as to be uninformative, 4) which were not considered to have significant clinical implications, or 5) which occurred at a rate equal to or less than placebo.

- Blood and Lymphatic System Disorders: thrombocytopenia
- Cardiac Disorders: bradycardia, sinus tachycardia, tachycardia
- Endocrine Disorders: hypoprolactinemia
- Eye Disorders: vision blurred, oculogyric crisis
- Gastrointestinal Disorders: abdominal pain upper, dyspepsia, nausea, swollen tongue
- General Disorders and Administration Site Conditions: chest discomfort, fatigue, gait disturbance, injection site reaction (erythema, induration, pruritus, swelling, rash, inflammation, hemorrhage), irritability, pyrexia
- Hepatobiliary Disorders: drug-induced liver injury
- Immune System Disorders: drug hypersensitivity
- Infections and Infestations: nasopharyngitis
- Investigations: blood creatine phosphokinase increased, blood cholesterol decreased, blood pressure decreased, blood triglycerides decreased, electrocardiogram T wave abnormal, electrocardiogram QT-prolonged, hepatic enzyme increased, liver function test abnormal
- Metabolism and Nutrition Disorders: decreased appetite, hyperinsulinemia, obesity
- Musculoskeletal and Connective Tissue Disorders: joint stiffness, muscle twitching, rhabdomyolysis, trismus
- Nervous System Disorders: bradykinesia, convulsion, dysgeusia, extrapyramidal disorder, hypersomnia, lethargy, memory impairment, oromandibular dystonia,
- Psychiatric Disorders: anxiety, insomnia, restlessness, agitation, bruxism, psychotic disorder, suicidal ideation, aggression, hypersexuality, panic attack
- Renal and Urinary Disorders: glycosuria, pollakiuria, urinary incontinence
- Reproductive System and Breast Disorders: ejaculation delayed
- Vascular Disorders: hypertension

Adverse Reactions Reported in Clinical Trials with Oral Aripiprazole

The following is a list of additional adverse reactions that have been reported in clinical trials with oral aripiprazole and not reported above for Abilify Maintena:

- Cardiac Disorders: angina pectoris, atrial flutter, atrioventricular block, cardiopulmonary failure, cardio-respiratory arrest, extrasystoles, myocardial infarction, myocardial ischemia, palpitations, supraventricular tachycardia, ventricular tachycardia
- Eye Disorders: diplopia, photophobia, eyelid edema, photopsia
- Gastrointestinal Disorders: gastroesophageal reflux disease, swollen tongue, esophagitis, pancreatitis, stomach discomfort, toothache
- General Disorders and Administration Site Conditions: asthenia, chest pain, face edema, hypothermia, peripheral edema, pain
- Hepatobiliary Disorders: hepatitis, jaundice
- Immune System Disorders: hypersensitivity
- Injury, Poisoning, and Procedural Complications: heat stroke
- Investigations: blood prolactin decreased, blood bilirubin increased, blood creatinine increased, blood glucose increased, blood lactate dehydrogenase increased, blood prolactin increased, blood urea increased, glycosylated hemoglobin increased
- Metabolism and Nutrition Disorders: anorexia, diabetic ketoacidosis, hyponatremia, hypoglycemia, polydipsia
- Musculoskeletal and Connective Tissue Disorders: mobility decreased, muscle rigidity, muscle tightness, muscular weakness, musculoskeletal stiffness, pain in extremity, muscle spasms
- Nervous System Disorders: akinesia, choreoathetosis, coordination abnormal, hypokinesia, hypotonia, myoclonus, speech disorder
- Psychiatric Disorders: anger, anorgasmia, catatonia, completed suicide, delirium, loss of libido, homicidal ideation, intentional self-injury, hostility, libido increased, sleepwalking, suicide attempt, tic
- Renal and Urinary Disorders: nocturia, polyuria, urinary retention
- Reproductive System and Breast Disorders: amenorrhea, breast pain, erectile dysfunction, gynecomastia, menstruation irregular, priapism
- Respiratory, Thoracic, and Mediastinal Disorders: dyspnea, nasal congestion, pharyngolaryngeal pain, cough
- Skin and Subcutaneous Tissue Disorders: alopecia, hyperhidrosis, photosensitivity reaction, pruritus, rash (including erythematous, exfoliative, generalized, macular, maculopapular, papular rash; acneiform, allergic, contact, exfoliative, seborrheic dermatitis, neurodermatitis, and drug eruption), urticaria

6.2 Postmarketing Experience

The following adverse reactions have been identified during post-approval use of aripiprazole. Because these reactions are reported voluntarily from a population of uncertain size, it is not always possible to reliably estimate their frequency or establish a causal relationship to drug exposure: occurrences of allergic reaction (anaphylactic reaction, angioedema, laryngospasm, pruritus/urticaria, or oropharyngeal spasm), blood glucose fluctuation, drug reaction with eosinophilia and systemic symptoms (DRESS), hiccups, pathological gambling, and fecal incontinence.

7 DRUG INTERACTIONS

7.1 Drugs Having Clinically Important Interactions with ABILIFY ASIMTUFII

Table 7 presents clinically significant drug interactions with ABILIFY ASIMTUFII.

Table 7: Clinically Important Drug Interactions with ABILIFY ASIMTUFII
Strong CYP3A4 Inhibitors AND/OR strong CYP2D6 inhibitors
Clinical Rationale | Concomitant use of oral aripiprazole with strong CYP3A4 AND/OR CYP2D6 inhibitors increased the exposure of aripiprazole [see Clinical Pharmacology (12.3)].
Clinical Recommendation | Concomitant use of a strong CYP3A4 inhibitor OR a strong CYP2D6 inhibitor Reduce the dosage of ABILIFY ASIMTUFII when administered concomitantly with a strong CYP3A4 inhibitor OR a strong CYP2D6 inhibitor for more than 14 days [see Dosage and Administration (2.4)]. Concomitant Use of a strong CYP3A4 inhibitor AND a strong CYP2D6 inhibitor Avoid use of ABILIFY ASIMTUFII when administered concomitantly with a strong CYP3A4 inhibitor AND a strong CYP2D6 inhibitor for more than 14 days [see Dosage and Administration (2.4)].
Strong CYP3A4 Inducers
Clinical Rationale | Concomitant use of oral aripiprazole and carbamazepine decreased the exposure of aripiprazole [see Clinical Pharmacology (12.3)].
Clinical Recommendation | Avoid use of ABILIFY ASIMTUFII in combination with a strong CYP3A4 inducer (e.g., carbamazepine) for greater than 14 days [see Dosage and Administration (2.4)].
Antihypertensive Drugs
Clinical Rationale | Due to its alpha-adrenergic antagonism, aripiprazole has the potential to enhance the effect of certain antihypertensive agents.
Clinical Recommendation | Monitor blood pressure and adjust dose accordingly [see Warnings and Precautions (5.7)].
Benzodiazepines
Clinical Rationale | The intensity of sedation was greater with the combination of oral aripiprazole and lorazepam as compared to that observed with aripiprazole alone. The orthostatic hypotension observed was greater with the combination as compared to that observed with lorazepam alone [see Warnings and Precautions (5.7)].
Clinical Recommendation | Monitor sedation and blood pressure. Adjust dose accordingly.

7.2 Drugs Having No Clinically Important Interactions with ABILIFY ASIMTUFII

Based on pharmacokinetic studies with oral aripiprazole, no dosage adjustment of ABILIFY ASIMTUFII is required when administered concomitantly with famotidine, valproate, lithium, lorazepam [see Clinical Pharmacology (12.3)].

In addition, no dosage adjustment is necessary for substrates of CYP2D6, CYP2C9, CYP2C19, or CYP3A4 when coadministered with ABILIFY ASIMTUFII. Additionally, no dosage adjustment is necessary for valproate, lithium, lamotrigine, lorazepam, or sertraline when coadministered with ABILIFY ASIMTUFII [see Clinical Pharmacology (12.3)].

8 USE IN SPECIFIC POPULATIONS

8.1 Pregnancy

Pregnancy Exposure Registry

There is a pregnancy exposure registry that monitors pregnancy outcomes in women exposed to atypical antipsychotics, including ABILIFY ASIMTUFII, during pregnancy. Healthcare providers are encouraged to register patients by contacting the National Pregnancy Registry for Atypical Antipsychotics at 1-866-961-2388 or visit http://womensmentalhealth.org/clinical-and-research-programs/pregnancyregistry/.

Risk Summary

Neonates exposed to antipsychotic drugs, including ABILIFY ASIMTUFII, during the third trimester of pregnancy are at risk for extrapyramidal and/or withdrawal symptoms (see Clinical Considerations). Overall available data from published epidemiologic studies of pregnant women exposed to aripiprazole have not established a drug-associated risk of major birth defects, miscarriage, or adverse maternal outcomes. There are risks to the mother associated with untreated schizophrenia or bipolar I disorder and with exposure to antipsychotics, including ABILIFY ASIMTUFII, during pregnancy (see Clinical Considerations). Aripiprazole exposure during pregnancy may decrease milk supply in the post-partum period [see Use in Specific Populations (8.2)].

In animal reproduction studies, oral and intravenous aripiprazole administration during organogenesis in rats and/or rabbits at doses 10 and 11 times, respectively, the maximum recommended human oral dose (MRHD) produced fetal death, decreased fetal weight, undescended testicles, delayed skeletal ossification, skeletal abnormalities, and diaphragmatic hernia. Oral and intravenous aripiprazole administration during the pre- and post-natal period in rats at doses 10 times the oral MRHD produced prolonged gestation, stillbirths, decreased pup weight, and decreased pup survival (see Data).

The background risk of major birth defects and miscarriage for the indicated population are unknown. All pregnancies have a background risk of birth defect, loss, or other adverse outcomes. In the U.S. general population, the estimated background risk of major birth defects and miscarriage in clinically recognized pregnancies is 2 to 4% and 15 to 20%, respectively.

Clinical Considerations

Disease-associated maternal and/or embryo/fetal risk

There is a risk to the mother from untreated schizophrenia or bipolar I disorder, including increased risk of relapse, hospitalization, and suicide. Schizophrenia and bipolar I disorder are associated with increased adverse perinatal outcomes, including preterm birth. It is not known if this is a direct result of the illness or other comorbid factors.

Fetal/Neonatal Adverse Reactions

Extrapyramidal and/or withdrawal symptoms, including agitation, hypertonia, hypotonia, tremor, somnolence, respiratory distress and feeding disorder have been reported in neonates who were exposed to antipsychotic drugs, including oral aripiprazole, during the third trimester of pregnancy. These symptoms have varied in severity. Some neonates recovered within hours or days without specific treatment; others required prolonged hospitalization. Monitor neonates exhibiting extrapyramidal and/or withdrawal symptoms and manage symptoms appropriately.

Data

Animal Data

No developmental toxicity studies were conducted with intramuscular aripiprazole suspension.

In animal oral or intravenous studies, aripiprazole demonstrated developmental toxicity, including possible teratogenic effects in rats and rabbits.

Pregnant rats were treated with oral doses of 3, 10, and 30 mg/kg/day which are approximately 1 to 10 times the oral MRHD of 30 mg/day on mg/m^2 basis of aripiprazole during the period of organogenesis. Treatment at the highest dose caused a slight prolongation of gestation and delay in fetal development, as evidenced by decreased fetal weight and undescended testes. Delayed skeletal ossification was observed at 3 and 10 times the oral MRHD on mg/m^2 basis.

At 3 and 10 times the oral MRHD on mg/m^2 basis, delivered offspring had decreased body weights. Increased incidences of hepatodiaphragmatic nodules and diaphragmatic hernia were observed in offspring from the highest dose group (the other dose groups were not examined for these findings). Postnatally, delayed vaginal opening was seen at 3 and 10 times the oral MRHD on mg/m^2 basis and impaired reproductive performance (decreased fertility rate, corpora lutea, implants, live fetuses, and increased post-implantation loss, likely mediated through effects on female offspring) along with some maternal toxicity were seen at the highest dose; however, there was no evidence to suggest that these developmental effects were secondary to maternal toxicity.

In pregnant rats treated with aripiprazole intravenously at doses of 3, 9, and 27 mg/kg/day, which are 1 to 9 times the oral MRHD on mg/m^2 basis, during the period of organogenesis, decreased fetal weight and delayed skeletal ossification were seen at the highest dose which also caused maternal toxicity.

In pregnant rabbits treated with oral doses of 10, 30, and 100 mg/kg/day which are 2 to 11 times human exposure at the oral MRHD based on AUC and 6 to 65 times the oral MRHD of aripiprazole on mg/m^2 basis during the period of organogenesis, decreased maternal food consumption and increased abortions were seen at the highest dose as well as increased fetal mortality. Decreased fetal weight and increased incidence of fused sternebrae were observed at 3 and 11 times the oral MRHD based on AUC.

In pregnant rabbits receiving aripiprazole injection intravenously at doses of 3, 10, and 30 mg/kg/day, which are 2 to 19 times the oral MRHD on mg/m^2 basis during the period of organogenesis, the highest dose caused pronounced maternal toxicity that resulted in decreased fetal weight, increased fetal abnormalities (primarily skeletal), and decreased fetal skeletal ossification. The fetal no-effect dose was 5 times the human exposure at the oral MRHD based on AUC and is 6 times the oral MRHD on mg/m^2 basis.

In rats treated with oral doses of 3, 10, and 30 mg/kg/day, which are 1 to 10 times the oral MRHD of aripiprazole on a mg/m^2 basis, peri- and post-natally (from Day 17 of gestation through Day 21 postpartum), slight maternal toxicity and slightly prolonged gestation were seen at the highest dose. An increase in stillbirths and decreases in pup weight (persisting into adulthood) and survival were also seen at this dose.

In rats treated with aripiprazole intravenously at doses of 3, 8, and 20 mg/kg/day which are 1 to 6 times the oral MRHD on mg/m^2 basis from Day 6 of gestation through Day 20 postpartum, increased stillbirths were seen at 3 and 6 times the oral MRHD on mg/m^2 basis, and decreases in early postnatal pup weight and survival were seen at the highest dose; these doses produced some maternal toxicity. There were no effects on postnatal behavioral and reproductive development.

8.2 Lactation

Risk Summary

Aripiprazole is present in human breast milk. Based on published case reports and pharmacovigilance reports, aripiprazole exposure during pregnancy and/or the postpartum period may lead to clinically relevant decreases in milk supply which may be reversible with discontinuation of the drug. There are also reports of aripiprazole exposure during pregnancy and no maternal milk supply in the post-partum period. Effects on milk supply may be mediated through decreases in prolactin levels, which have been observed [see Adverse Reactions (6.1)]. Monitor the breastfed infant for dehydration and lack of appropriate weight gain. The developmental and health benefits of breastfeeding should be considered along with the mother's clinical need for ABILIFY ASIMTUFII and any potential adverse effects on the breastfed infant from ABILIFY ASIMTUFII or from the underlying maternal condition.

8.4 Pediatric Use

Safety and effectiveness of ABILIFY ASIMTUFII in pediatric patients have not been established.

Juvenile Animal Studies

No juvenile animal studies were conducted with intramuscular aripiprazole suspension. A study with oral aripiprazole in juvenile rats caused mortality, CNS clinical signs, impaired memory and learning, and delayed sexual maturation when administered at doses of 10, 20, 40 mg/kg/day from weaning (21 days old) through maturity (80 days old). At 40 mg/kg/day, mortality, decreased activity, splayed hind limbs, hunched posture, ataxia, tremors and other CNS signs were observed in both genders. In addition, delayed sexual maturation was observed in males. At all doses and in a dose-dependent manner, impaired memory and learning, increased motor activity, and histopathology changes in the pituitary (atrophy), adrenals (adrenocortical hypertrophy), mammary glands (hyperplasia and increased secretion), and female reproductive organs (vaginal mucification, endometrial atrophy, decrease in ovarian corpora lutea) were observed. The changes in female reproductive organs were considered secondary to the increase in prolactin serum levels. A No Observed Adverse Effect Level (NOAEL) could not be determined and, at the lowest tested dose of 10 mg/kg/day, there is no safety margin relative to the systemic exposures (AUC0-24) for aripiprazole or its major active metabolite in adolescents at the maximum recommended oral pediatric dose of 15 mg/day. All drug-related effects were reversible after a 2-month recovery period, and most of the drug effects in juvenile rats were also observed in adult rats from previously conducted studies.

Aripiprazole in juvenile dogs (2 months old) caused CNS clinical signs of tremors, hypoactivity, ataxia, recumbency and limited use of hind limbs when administered orally for 6 months at 3, 10, 30 mg/kg/day. Mean body weight and weight gain were decreased up to 18% in females in all drug groups relative to control values. A NOAEL could not be determined and, at the lowest tested dose of 3 mg/kg/day, there is no safety margin relative to the systemic exposures (AUC0-24) for aripiprazole or its major active metabolite in adolescents at the maximum recommended oral pediatric dose of 15 mg/day. All drug-related effects were reversible after a 2-month recovery period.

8.5 Geriatric Use

Clinical studies of ABILIFY ASIMTUFII did not include sufficient numbers of subjects aged 65 years and over to determine whether they respond differently from younger subjects. Other reported clinical experience and pharmacokinetic data have not identified differences in responses between the elderly and younger patients [see Clinical Pharmacology (12.3)]. In general, dose selection for an elderly patient should be cautious, usually starting at the low end of the dosing range, reflecting the greater frequency of decreased hepatic, renal, or cardiac function, and of concomitant disease or other drug therapy.

In single-dose and multiple-dose pharmacokinetic studies with oral aripiprazole, there was no detectable age effect in the population pharmacokinetic analysis in schizophrenia patients [see Clinical Pharmacology (12.3)]. No dosage adjustments are recommended based on age alone. ABILIFY ASIMTUFII is not approved for the treatment of patients with dementia-related psychosis [see also Boxed Warning and Warnings and Precautions (5.1)].

8.6 CYP2D6 Poor Metabolizers

Dosage adjustment is recommended in known CYP2D6 poor metabolizers due to high aripiprazole concentrations. Approximately 8% of Caucasians and 3% to 8% of Black/African Americans cannot metabolize CYP2D6 substrates and are classified as poor metabolizers (PM) [see Dosage and Administration (2.4)].

10 OVERDOSAGE

Human Experience

Common adverse reactions (reported in at least 5% of all overdose cases) reported with oral aripiprazole overdosage (alone or in combination with other substances) include vomiting, somnolence, and tremor. Other clinically important signs and symptoms observed in one or more patients with aripiprazole overdoses (alone or with other substances) include acidosis, aggression, aspartate aminotransferase increased, atrial fibrillation, bradycardia, coma, confusional state, convulsion, blood creatine phosphokinase increased, depressed level of consciousness, hypertension, hypokalemia, hypotension, lethargy, loss of consciousness, QRS complex prolonged, QT prolonged, pneumonia aspiration, respiratory arrest, status epilepticus, and tachycardia.

Management of Overdosage

In case of overdosage, call the Poison Control Center immediately at 1-800-222-1222 or medical toxicologist for additional overdosage management recommendations.

11 DESCRIPTION

Aripiprazole is an atypical antipsychotic which is present in ABILIFY ASIMTUFII as its monohydrate polymorphic form. Aripiprazole monohydrate is 7-[4-[4-(2,3-dichlorophenyl)-1-piperazinyl] butoxy]-3,4 dihydrocarbostyril monohydrate. The empirical formula is C23H27Cl2N3O2∙H2O and its molecular weight is 466.40. The chemical structure is:

ABILIFY ASIMTUFII (aripiprazole) is available as a white to off-white, sterile, aqueous extended-release suspension for intramuscular injection in 720 mg or 960 mg dose strength, pre-filled syringes. The labeled strengths are calculated based on the anhydrous form (aripiprazole). Inactive ingredients are carboxymethylcellulose sodium (5 mg/mL), polyethylene glycol 400 (1 mg/mL), povidone (4 mg/mL), sodium chloride (6.1 mg/mL), sodium phosphate monobasic monohydrate (0.74 mg/mL), sodium hydroxide (to adjust pH) and water for injection (q.s.).

12 CLINICAL PHARMACOLOGY

12.1 Mechanism of Action

The mechanism of action of aripiprazole in the treatment of schizophrenia and bipolar I disorder is unknown.

The efficacy of aripiprazole could be mediated through a combination of partial agonist activity at dopamine D2 and serotonin 5-HT1A receptors and antagonist activity at 5-HT2A receptors.

12.2 Pharmacodynamics

Aripiprazole exhibits high affinity for dopamine D2 and D3 (Kis 0.34 and 0.8 nM, respectively), serotonin 5-HT1A and 5-HT2A receptors (Kis 1.7 and 3.4 nM, respectively), moderate affinity for dopamine D4, serotonin 5-HT2C and 5-HT7, alpha1-adrenergic and histamine H1 receptors (Kis of 44 nM, 15 nM, 39 nM, 57 nM, and 61 nM, respectively), and moderate affinity for the serotonin reuptake site (Ki=98 nM). Aripiprazole has no appreciable affinity for cholinergic muscarinic receptors (IC50>1000 nM). Actions at receptors other than D2, 5-HT1A, and 5-HT2A could explain some of the other adverse reactions of aripiprazole (e.g., the orthostatic hypotension observed with aripiprazole may be explained by its antagonist activity at adrenergic alpha1 receptors).

ABILIFY ASIMTUFII activity is presumably primarily due to the parent drug, aripiprazole, and to a lesser extent, to its major metabolite, dehydro-aripiprazole, which has been shown to have affinities for D2 receptors.

12.3 Pharmacokinetics

ABILIFY ASIMTUFII delivers aripiprazole over a 2-month period. ABILIFY ASIMTUFII has linear pharmacokinetics in the approved dose range. Steady-state aripiprazole exposures were reached by the fourth dose. Plasma exposures at steady state were compared between ABILIFY ASIMTUFII (960 mg, once every 2 months) and Abilify Maintena (400 mg, once every month). The average plasma concentrations (Cavg) of aripiprazole were 263 ng/mL and 280 ng/mL for ABILIFY ASIMTUFII and Abilify Maintena, respectively. The Cmax of aripiprazole were 342 ng/mL and 344 ng/mL for ABILIFY ASIMTUFII and Abilify Maintena, respectively.

Figure 9: Mean Plasma Concentration of Aripiprazole Following the Fourth Administration of ABILIFY ASIMTUFII 960 mg versus the Seventh and Eighth Administration of Abilify Maintena 400 mg

Absorption

Aripiprazole absorption into the systemic circulation is prolonged following gluteal intramuscular injection due to low solubility of aripiprazole particles. The release profile of aripiprazole from ABILIFY ASIMTUFII results in sustained plasma concentrations over 2 months following gluteal injection(s). Following multiple doses, the median peak:trough ratio for aripiprazole following an ABILIFY ASIMTUFII dose is 1.3, resulting in a flat plasma concentration profile with Tmax ranging between 1 to 49 days following multiple gluteal administrations of 960 mg.

Distribution

Based on results from trials with oral administration of aripiprazole, aripiprazole is widely distributed throughout the body with an apparent volume of distribution of 4.9 L/kg, indicating extensive extravascular distribution. At therapeutic concentrations, aripiprazole and dehydro-aripiprazole are greater than 99% bound to serum proteins, binding primarily to albumin.

Elimination

Following single dose administration of ABILIFY ASIMTUFII, the mean apparent terminal elimination half-life of aripiprazole was 21 days.

Metabolism

Aripiprazole is metabolized primarily by three biotransformation pathways: dehydrogenation, hydroxylation, and N-dealkylation. Based on in vitro studies, CYP3A4 and CYP2D6 enzymes are responsible for dehydrogenation and hydroxylation of aripiprazole, and N-dealkylation is catalyzed by CYP3A4. Aripiprazole is the predominant drug moiety in the systemic circulation. Following administration of multiple doses of ABILIFY ASIMTUFII, dehydro-aripiprazole, the active metabolite, represents approximately 29% of aripiprazole AUC in plasma.

Excretion

Following a single oral dose of [14C]-labeled aripiprazole, approximately 25% and 55% of the administered radioactivity was recovered in the urine and feces, respectively. Less than 1% of unchanged aripiprazole was excreted in the urine and approximately 18% of the oral dose was recovered unchanged in the feces.

Studies in Specific Populations

No specific pharmacokinetic studies have been performed with ABILIFY ASIMTUFII in specific populations. All the information is obtained from studies with oral aripiprazole or is based on the pharmacokinetic modeling of oral aripiprazole and/or ABILIFY ASIMTUFII.

Exposures of aripiprazole and dehydro-aripiprazole in specific populations are summarized in Figure 10 and Figure 11, respectively. In addition, in pediatric patients (10 to 17 years of age) administered with oral aripiprazole (20 mg to 30 mg), the body weight corrected aripiprazole clearance was similar to the adults.

Figure 10: Effect of Intrinsic Factors on Aripiprazole Pharmacokinetics

Figure 11: Effects of Intrinsic Factors on Dehydro-aripiprazole Pharmacokinetics

Drug Interaction Studies

No specific drug interaction studies have been performed with ABILIFY ASIMTUFII. The information below is obtained from studies with oral aripiprazole.

The effect of other drugs on the exposures of aripiprazole and dehydro-aripiprazole are summarized in Figure 12 and Figure 13, respectively. Based on simulations, a 4.5-fold increase in mean Cmax and AUC values at steady-state is expected when extensive metabolizers of CYP2D6 are administered with both strong CYP2D6 and CYP3A4 inhibitors. After oral administration, a 3-fold increase in mean Cmax and AUC values at steady-state is expected in poor metabolizers of CYP2D6 administered with strong CYP3A4 inhibitors.

Figure 12: The Effect of Other Drugs on Aripiprazole Pharmacokinetics

Figure 13: The Effect of Other Drugs on Dehydro-aripiprazole Pharmacokinetics

The effect of oral aripiprazole on the exposures of other drugs are summarized in Figure 14. A population PK analysis in patients with major depressive disorder showed no substantial change in plasma concentrations of fluoxetine (20 mg/day or 40 mg/day), paroxetine CR (37.5 mg/day or 50 mg/day), or sertraline (100 mg/day or 150 mg/day) dosed to steady-state. The steady-state plasma concentrations of fluoxetine and norfluoxetine increased by about 18% and 36%, respectively, and concentrations of paroxetine decreased by about 27%. The steady-state plasma concentrations of sertraline and desmethylsertraline were not substantially changed when these antidepressant therapies were coadministered with aripiprazole.

Figure 14: The Effect of Oral Aripiprazole on Pharmacokinetics of Other Drugs

In vitro

Aripiprazole is not a substrate of CYP1A1, CYP1A2, CYP2A6, CYP2B6, CYP2C8, CYP2C9, CYP2C19, or CYP2E1 enzymes. Aripiprazole also does not undergo direct glucuronidation.

13 NONCLINICAL TOXICOLOGY

13.1 Carcinogenesis, Mutagenesis, Impairment of Fertility

Carcinogenesis

No carcinogenicity studies were conducted with intramuscular aripiprazole suspension.

Lifetime carcinogenicity studies were conducted with oral aripiprazole in Swiss albino mice, Sprague-Dawley (SD) rats, and F344 rats. Oral aripiprazole was administered for 2 years in the diet at doses of 1, 3, 10, and 30 mg/kg/day to ICR mice and 1, 3, and 10 mg/kg/day to F344 rats (0.2 to 5 times and 0.3 to 3 times oral MRHD based on mg/m^2, respectively). In addition, SD rats were dosed orally for 2 years at 10, 20, 40, and 60 mg/kg/day (3 to 19 times the oral MRHD based on mg/m^2). Aripiprazole did not induce tumors in male mice or male rats. In female mice, the incidence of pituitary gland adenomas, mammary gland adenocarcinomas and adenoacanthomas were increased at dietary doses of 3 to 30 mg/kg/day (0.5 to 5 times the oral MRHD based on mg/m^2). In female rats, the incidence of mammary gland fibroadenomas was increased at a dietary dose of 10 mg/kg/day (3 times the oral MRHD based on mg/m^2); and the incidences of adrenocortical carcinomas and combined adrenocortical adenomas/carcinomas were increased at an oral dose of 60 mg/kg/day (19 times the oral MRHD based on mg/m^2).

Proliferative changes in the pituitary and mammary gland of rodents have been observed following chronic administration of other antipsychotic agents and are considered prolactin-mediated. Serum prolactin was not measured in the aripiprazole carcinogenicity studies. However, increases in serum prolactin levels were observed in female mice in a 13-week dietary study at the doses associated with mammary gland and pituitary tumors. Serum prolactin was not increased in female rats in 4-week and 13-week dietary studies at the dose associated with mammary gland tumors. The relevance for human risk of the findings of prolactin-mediated endocrine tumors in rodents is unknown.

Mutagenesis

The mutagenic potential of aripiprazole was tested in the in vitro bacterial reverse-mutation assay, the in vitro bacterial DNA repair assay, the in vitro forward gene mutation assay in mouse lymphoma cells, the in vitro chromosomal aberration assay in Chinese hamster lung (CHL) cells, the in vivo micronucleus assay in mice, and the unscheduled DNA synthesis assay in rats. Aripiprazole and a metabolite (2,3-DCPP) were clastogenic in the in vitro chromosomal aberration assay in CHL cells with and without metabolic activation. The metabolite, 2,3-DCPP, produced increases in numerical aberrations in the in vitro assay in CHL cells in the absence of metabolic activation. A positive response was obtained in the in vivo micronucleus assay in mice; however, the response was due to a mechanism not considered relevant to humans.

Impairment of Fertility

No mating and fertility studies were conducted with intramuscular aripiprazole suspension.

Female rats were treated with aripiprazole oral doses of 2, 6, and 20 mg/kg/day (0.6, 2, and 6 times the oral MRHD on a mg/m^2 basis) of aripiprazole from 2 weeks prior to mating through Day 7 of gestation. Estrus cycle irregularities and increased corpora lutea were seen at all doses, but no impairment of fertility was seen. Increased pre-implantation loss was seen at 6 and 20 mg/kg/day and decreased fetal weight was seen at 20 mg/kg/day.

Male rats were treated with oral doses of 20, 40, and 60 mg/kg/day (6, 13, and 19 times the oral MRHD on mg/m^2 basis) of aripiprazole from 9 weeks prior to mating through mating. Disturbances in spermatogenesis were seen at 60 mg/kg and prostate atrophy was seen at 40 and 60 mg/kg, but no impairment of fertility was seen.

13.2 Animal Toxicology and/or Pharmacology

The toxicological profile for aripiprazole administered to experimental animals by intramuscular injection is generally similar to that seen following oral administration at comparable plasma levels of the drug. In dogs, repeated intramuscular dosing of the 2-month aripiprazole extended release injectable suspension over a period of 52 weeks produced no clinical evidence of significant local irritation, and resulted in slight foreign-body type of localized granulomatous inflammatory reaction to deposited drug at the injection site. These effects gradually resolved with discontinuation of dosing.

Oral aripiprazole produced retinal degeneration in albino rats in a 26-week chronic toxicity study at a dose of 60 mg/kg and in a 2-year carcinogenicity study at doses of 40 and 60 mg/kg. The 40 and 60 mg/kg/day doses are 13 and 19 times the maximum recommended human oral dose (MRHD) based on mg/m^2 body surface and 7 to 14 times human exposure at the oral MRHD based on AUC. Evaluation of the retinas of albino mice and of monkeys did not reveal evidence of retinal degeneration. Additional studies to further evaluate the mechanism have not been performed. The relevance of this finding to human risk is unknown.

14 CLINICAL STUDIES

14.1 Schizophrenia

The efficacy of ABILIFY ASIMTUFII (once every 2 month dosing) for the treatment of schizophrenia in adults is based on adequate and well-controlled studies of Abilify Maintena (once monthly dosing). The results of these adequate and well-controlled studies are presented below.

The efficacy of Abilify Maintena (once monthly dosing) for treatment of schizophrenia was established in:

• One short-term (12-week), randomized, double-blind, placebo-controlled trial in acutely relapsed adults (Study 1)

• One longer-term, double-blind, placebo-controlled, randomized-withdrawal (maintenance) trial in adults (Study 2).

Short-Term Efficacy

In the short-term (12-week), randomized, double-blind, placebo-controlled trial in acutely relapsed adults (Study 1), the primary measure used for assessing psychiatric signs and symptoms was the Positive and Negative Syndrome Scale (PANSS). The PANSS is a 30-item scale that measures positive symptoms of schizophrenia (7 items), negative symptoms of schizophrenia (7 items), and general psychopathology (16 items), each rated on a scale of 1 (absent) to 7 (extreme); total PANSS scores range from 30 to 210. The primary endpoint was the change from baseline in PANSS total score to week 10.

The inclusion criteria for this short-term trial included adult inpatients who met DSM-IV-TR criteria for schizophrenia. In addition, all patients entering the trial must have experienced an acute psychotic episode as defined by both PANSS Total Score ≥80 and a PANSS score of >4 on each of four specific psychotic symptoms (conceptual disorganization, hallucinatory behavior, suspiciousness/persecution, unusual thought content) at screening and baseline. The key secondary endpoint was the change from baseline in Clinical Global Impression-Severity (CGI-S) assessment scale to week 10. The CGI-S rates the severity of mental illness on a scale of 1 (normal) to 7 (among the most extremely ill) based on the total clinical experience of the rater in treating patients with schizophrenia. Patients had a mean PANSS total score of 103 (range 82 to 144) and a CGI-S score of 5.2 (markedly ill) at entry.

In this 12-week study (n=339) comparing Abilify Maintena (n=167) to placebo (n=172), patients were administered 400 mg Abilify Maintena or placebo on days 0, 28, and 56. The dose could be adjusted down and up within the range of 400 to 300 mg on a one-time basis. Abilify Maintena was superior to placebo in improving the PANSS total score at the end of week 10 (see Table 8).

Table 8: Efficacy Results of Abilify Maintena in Short-term Schizophrenia Study 1 (Adults)
 |  | Primary Efficacy Measure: PANSS Total Score
Study Number | Treatment Group | Mean Baseline Score (SD) | LS Mean Change from Baseline (SE) | Placebo-subtracted Difference [Difference (drug minus placebo) in least-squares mean change from baseline.] (95% CI)
Study 1 | Abilify Maintena (400 to 300 mg) | 102.4 (11.4) | -26.8 (1.6) | -15.1 (-19.4, -10.8)
Study 1 | Placebo | 103.4 (11.1) | -11.7 (1.6) | --
SD: standard deviation; SE: standard error; LS Mean: least-squares mean; CI: unadjusted confidence interval.

The change in PANSS total score by week is shown in Figure 15. Abilify Maintena also showed improvement in symptoms represented by CGI-S score mean change from baseline to week 10. The results of exploratory subgroup analyses by gender, race, age, ethnicity, and BMI were similar to the results of the overall population.

Figure 15: Weekly PANSS Total Score-Change in the 12-Week, Placebo-Controlled Study with Abilify Maintena in Schizophrenia - Study 1 (Adults)

n = the number of patients remaining in the respective study arm at each time point

Long-Term Efficacy

The efficacy of Abilify Maintena in maintaining symptomatic control in schizophrenia was established in a double-blind, placebo-controlled, randomized-withdrawal trial in adult patients (Study 2) who met DSM-IV-TR criteria for schizophrenia and who were being treated with at least one antipsychotic medication. Patients had at least a 3-year history of illness and a history of relapse or symptom exacerbation when not receiving antipsychotic treatment.

In addition to the PANSS and CGI-S, clinical ratings during this trial included the:

- Clinical Global Impression-Improvement (CGI-I) scale, a scale of 1 (very much improved) to 7 (very much worse) based on the change from baseline in clinical condition and
- Clinical Global Impression-Severity of Suicide (CGI-SS) scale, which is comprised of 2 parts: Part 1 rates the severity of suicidal thoughts and behavior on a scale of 1 (not at all suicidal) to 5 (attempted suicide) based on the most severe level in the last 7 days from all information available to the rater and Part 2 rates the change from baseline in suicidal thoughts and behavior on a scale of 1 (very much improved) to 7 (very much worse).

This trial included:

- A 4 to 6 week open-label, oral conversion phase for patients on antipsychotic medications other than aripiprazole. A total of 633 patients entered this phase.
- An open-label, oral aripiprazole stabilization phase (target dose of 10 mg to 30 mg once daily). A total of 710 patients entered this phase. Patients were 18 to 60 years old (mean 40 years) and 60% were male. The mean PANSS total score was 66 (range 33 to 124). The mean CGI-S score was 3.5 (mildly to moderately ill). Prior to the next phase, stabilization was required. Stabilization was defined as having all of the following for four consecutive weeks: an outpatient status, PANSS total score ≤80, CGI-S ≤4 (moderately ill), and CGISS score ≤2 (mildly suicidal) on Part 1 and ≤5 (minimally worsened) on Part 2; and a score of ≤4 on each of the following PANSS items: conceptual disorganization, suspiciousness, hallucinatory behavior, and unusual thought content.
- A minimum 12-week uncontrolled, single-blind Abilify Maintena stabilization phase (treatment with 400 mg of Abilify Maintena given every 4 weeks in conjunction with oral aripiprazole [10 mg to 20 mg/day] for the first 2 weeks). The dose of Abilify Maintena may have been decreased to 300 mg due to adverse reactions. A total of 576 patients entered this phase. The mean PANSS total score was 59 (range 30 to 80) and the mean CGI-S score was 3.2 (mildly ill). Prior to the next phase, stabilization was required (see above for the definition of stabilization) for 12 consecutive weeks.
- A double-blind, placebo-controlled randomized-withdrawal phase to observe for relapse (defined below). A total of 403 patients were randomized 2:1 to the same dose of Abilify Maintena they were receiving at the end of the stabilization phase, (400 mg or 300 mg administered once every 4 weeks) or placebo. Patients had a mean PANSS total score of 55 (range 31 to 80) and a CGI-S score of 2.9 (mildly ill) at entry. The dose could be adjusted up and down or down and up within the range of 300 to 400 mg on a one-time basis.

The primary efficacy endpoint was time from randomization to relapse. Relapse was defined as the first occurrence of one or more of the following criteria:

- CGI-I of ≥5 (minimally worse) and
  1. an increase on any of the following individual PANSS items (conceptual disorganization, hallucinatory behavior, suspiciousness, unusual thought content) to a score >4 with an absolute increase of ≥2 on that specific item since randomization or
  2. an increase on any of the following individual PANSS items (conceptual disorganization, hallucinatory behavior, suspiciousness, unusual thought content) to a score >4 and an absolute increase ≥4 on the combined four PANSS items (conceptual disorganization, hallucinatory behavior, suspiciousness, unusual thought content) since randomization
- Hospitalization due to worsening of psychotic symptoms (including partial hospitalization), but excluding hospitalization for psychosocial reasons
- CGI-SS of 4 (severely suicidal) or 5 (attempted suicide) on Part 1 and/or 6 (much worse) or 7 (very much worse) on Part 2, or
- Violent behavior resulting in clinically significant self-injury, injury to another person, or property damage.

A pre-planned interim analysis demonstrated a statistically significantly longer time to relapse in patients randomized to the Abilify Maintena group compared to placebo-treated patients and the trial was subsequently terminated early because maintenance of efficacy was demonstrated. The final analysis demonstrated a statistically significantly longer time to relapse in patients randomized to the Abilify Maintena group than compared to placebo-treated patients. The Kaplan-Meier curves of the cumulative proportion of patients with relapse during the double-blind treatment phase for Abilify Maintena and placebo groups are shown in Figure 16.

Figure 16: Kaplan-Meier Estimation of Cumulative Proportion of Abilify Maintena-Treated Patients with Relapse [This figure is based on a total of 80 relapse events.] (Adults) Study 2

The key secondary efficacy endpoint, percentage of patients meeting the relapse criteria, was statistically significantly lower in patients randomized to the Abilify Maintena group (10%) than in the placebo group (40%).

14.2 Bipolar I Disorder - Maintenance Monotherapy

The efficacy of ABILIFY ASIMTUFII (once every 2 month dosing) for the treatment of maintenance monotherapy treatment of bipolar I disorder in adults is based on an adequate and well-controlled study of Abilify Maintena (once monthly dosing). The results of the adequate and well-controlled study are presented below.

The efficacy of Abilify Maintena (once monthly dosing) for the maintenance treatment of bipolar I disorder was established in a 52-week, double-blind, placebo-controlled, randomized withdrawal trial in adult patients who were experiencing a manic episode at trial entry, met DSM-IV-TR criteria for bipolar I disorder, and had a history of at least one previous manic or mixed episode with manic symptoms of sufficient severity to require one of the following interventions: hospitalization and/or treatment with a mood stabilizer, and/or treatment with an antipsychotic agent.

Clinical ratings during this trial included:

Young Mania Rating Scale (YMRS)-an 11-item, clinician-rated scale used to assess the degree of manic symptomatology, in a range with 0 representing no symptoms, and 60 representing worst symptoms; Montgomery-Asberg Depression Rating Scale (MADRS) – a 10-item clinician-related scale used to assess the degree of depressive symptomatology, with 1 representing no symptoms, and 60 representing worst symptoms; Clinical Global Impression Bipolar Version Severity of Illness (CGI-BP-S) a scale of 1 (normal, not at all ill) to 7 (very severely ill patient) based on the patient's severity of illness mania, depression, and overall bipolar illness.

This trial included:

- A 4 to 6 week, open-label, oral conversion phase for patients on treatments for bipolar I disorder other than aripiprazole. A total of 466 patients entered this phase.
- A 2 to 8 week, open-label, oral aripiprazole stabilization phase (target dose of 15 mg to 30 mg once daily). A total of 632 patients entered this phase. Patients were 18 to 65 years old (mean 40.7 years) and 60% were female. The mean (range) baseline scores were: YMRS total, 16.9 MADRS total, 5.7, and CGI-BP-S overall, 3.4 (mildly to moderately ill). Prior to the next phase, stabilization was required. Stabilization was defined as having all of the following at one bi-weekly visit: Outpatient status, YMRS total score ≤12, MADRS total score ≤12 no active suicidality; with active suicidality defined as a score of 4 or more on the MADRS item 10 OR an answer of "yes" on question 4 or 5 on the Columbia Suicide Severity Rating Scale (C-SSRS).
- A minimum 12-week, uncontrolled, single-blind Abilify Maintena stabilization phase (treatment with 400 mg of Abilify Maintena given every 4 weeks in conjunction with oral aripiprazole [10 mg to 20 mg/day] for the first 2 weeks). The dose of Abilify Maintena was allowed to be decreased to 300 mg due to adverse reactions. A total of 425 patients entered this phase. The mean (range) baseline scores were: YMRS total, 5.8, MADRS total 3.7, and CGI-BP-S overall, 2.1 (minimally ill). Prior to the next phase, stabilization was required (see above for the definition of stabilization) for 8 consecutive weeks starting at week 6.
- A double-blind, placebo-controlled, randomized-withdrawal phase to observe for recurrence to a mood episode (defined below) for up to 52 weeks. A total of 266 patients were randomized 1:1 to the same dose of Abilify Maintena they were receiving at the end of the stabilization phase, (400 mg or 300 mg administered once every 4 weeks) or placebo. The mean (range) baseline scores were: YMRS total, 2.8 (0 to 12), MADRS total, 2.7 (0 to 12), and CGI-S overall, 1.7 (minimally ill). The dose could be decreased to 300 mg for tolerability and returned once to 400 mg.

The primary efficacy endpoint was time from randomization to recurrence of any mood episode. Recurrence was defined as the first occurrence of one or more of the following criteria:

1) Hospitalization for any mood episode OR 2) Any of the following: a. YMRS total score ≥15 OR b. MADRS total score ≥15 OR c. Clinical Global Impression - Bipolar Version-Severity (CGI-BP-S) score >4 (overall score) OR 3) Serious adverse event (SAE) of worsening disease (bipolar I disorder) OR 4) Discontinuation due to lack of efficacy or discontinuation due to an adverse event (AE) of worsening disease OR 5) Clinical worsening with the need for addition of a mood stabilizer, antidepressant treatment, antipsychotic medication, and/or increase greater than the allowed benzodiazepine doses for treatment of symptoms of an underlying mood disorder OR 6) Active suicidality, which is defined as a score of 4 or more on the MADRS item 10 OR an answer of "yes" on question 4 or 5 on the C-SSRS

Analysis demonstrated a statistically significantly longer time to recurrence of any mood episode in subjects randomized to the Abilify Maintena group than compared to placebo-treated subjects. The Kaplan-Meier curves of the time of recurrence to any mood episode during the double-blind treatment phase for Abilify Maintena and placebo groups are shown in Figure 17.

Figure 17: Kaplan-Meier Estimation of Cumulative Recurrence Rate for Any Mood Episode [This figure is based on a total of 103 recurrence events.] in Abilify Maintena-Treated Adults

Analysis by type of mood recurrence demonstrated a statistically significantly longer time to recurrence for both manic and mixed mood episodes in subjects treated with Abilify Maintena compared to those treated with placebo. There was no substantial difference between treatment groups in delaying time to recurrence of depressive mood episodes.

An examination of subgroups did not reveal any clear evidence of differential responsiveness on the basis of age, sex, or race.

16 HOW SUPPLIED/STORAGE AND HANDLING

How Supplied

ABILIFY ASIMTUFII (aripiprazole) is available as white to off-white, sterile aqueous extended-release injectable suspension in single-dose, pre-filled syringes in 720 mg/2.4 mL or 960 mg/3.2 mL strengths.

The single-use kit contains 1 pre-filled syringe and 2 safety needles (a 1.5 inch 22 gauge needle and a 2 inch 21 gauge needle).

- 720 mg aripiprazole kit with aqua colored syringe tip wrap (NDC 59148-102-80)
- 960 mg aripiprazole kit with light blue colored syringe tip wrap (NDC 59148-114-80)

Storage

Store at 25°C (77°F), excursions permitted between 15° and 30°C (59° to 86°F) [see USP Controlled Room Temperature].

17 PATIENT COUNSELING INFORMATION

Advise the patient to read the FDA-approved patient labeling (Medication Guide)

Neuroleptic Malignant Syndrome

Counsel patients about a potentially fatal adverse reaction, Neuroleptic Malignant Syndrome (NMS) that has been reported in association with administration of antipsychotic drugs. Advise patients, family members, or caregivers to contact a health care provider or report to the emergency room if they experience signs and symptoms of NMS [see Warnings and Precautions (5.3)].

Tardive Dyskinesia

Counsel patients on the signs and symptoms of tardive dyskinesia and to contact their health care provider if these abnormal movements occur [see Warnings and Precautions (5.4)].

Metabolic Changes

Educate patients about the risk of metabolic changes, how to recognize symptoms of hyperglycemia and diabetes mellitus, and the need for specific monitoring, including blood glucose, lipids, and weight [see Warnings and Precautions (5.5)].

Pathological Gambling and Other Compulsive Behaviors

Advise patients and their caregivers of the possibility that they may experience compulsive urges to shop, increased urges to gamble, compulsive sexual urges, binge eating and/or other compulsive urges and the inability to control these urges while taking ABILIFY ASIMTUFII. In some cases, but not all, the urges were reported to have stopped when the dose was reduced or stopped [see Warnings and Precautions (5.6)].

Orthostatic Hypotension and Syncope

Educate patients about the risk of orthostatic hypotension and syncope, especially early in treatment, and also at times of re-initiating treatment or increases in dosage [see Warnings and Precautions (5.7)].

Leukopenia/Neutropenia

Advise patients with a pre-existing low WBC count or a history of drug-induced leucopenia/neutropenia that they should have their CBC monitored while receiving ABILIFY ASIMTUFII [see Warnings and Precautions (5.9)].

Potential for Cognitive and Motor Impairment

Inform patients that ABILIFY ASIMTUFII has the potential to impair judgment, thinking, or motor skills. Caution patients about performing activities requiring mental alertness, such as operating hazardous machinery or operating a motor vehicle, until they are reasonably certain that ABILIFY ASIMTUFII therapy does not affect them adversely [see Warnings and Precautions (5.11)].

Heat Exposure and Dehydration

Educate patients regarding appropriate care in avoiding overheating and dehydration [see Warnings and Precautions (5.12)].

Concomitant Medication

Advise patients to inform their health care providers of any changes to their current prescription or over-the-counter medications because there is a potential for clinically significant interactions [see Drug Interactions (7.1)].

Pregnancy

Advise patients to notify their healthcare provider if they become pregnant or intend to become pregnant during treatment with ABILIFY ASIMTUFII. Advise patients that ABILIFY ASIMTUFII may cause extrapyramidal and/or withdrawal symptoms (agitation, hypertonia, hypotonia, tremor, somnolence, respiratory distress, and feeding disorder) in a neonate. Advise patients that there is a pregnancy exposure registry that monitors pregnancy outcomes in women exposed to ABILIFY ASIMTUFII during pregnancy [see Use in Specific Populations (8.1)].

Lactation

ABILIFY ASIMTUFII use during pregnancy may affect milk supply. Advise the lactating patient to discuss any plans for breastfeeding with their healthcare provider, and to monitor the breastfed infant for dehydration and lack of appropriate weight gain [see Use in Specific Populations (8.2)].

Distributed and marketed by Otsuka America Pharmaceutical, Inc., Rockville, MD 20850 USA

Marketed by Lundbeck, Deerfield, IL 60015 USA

ABILIFY ASIMTUFII is a trademark of Otsuka Pharmaceutical Co., Ltd.

©2025, Otsuka Pharmaceutical Co., Ltd., 2-9 Kanda-Tsukasamachi, Chiyoda-ku, Tokyo, 101-8535 Japan

MEDICATION GUIDE
ABILIFY ASIMTUFII® (a-BIL-i-fy AH-SIM-TUH-FYE)
(aripiprazole) for extended-release injectable suspension, for intramuscular use

What is the most important information I should know about ABILIFY ASIMTUFII?
ABILIFY ASIMTUFII may cause serious side effects, including:

- Increased risk of death in elderly people with dementia-related psychosis. ABILIFY ASIMTUFII increases the risk of death in elderly people who have lost touch with reality (psychosis) due to confusion and memory loss (dementia). ABILIFY ASIMTUFII is not for the treatment of people with dementia-related psychosis.

What is ABILIFY ASIMTUFII?
ABILIFY ASIMTUFII is a prescription medicine given by injection by a healthcare provider:

- for the treatment of schizophrenia in adults
- alone as maintenance treatment of bipolar I disorder in adults

It is not known if ABILIFY ASIMTUFII is safe and effective in children under 18 years of age.

Who should not receive ABILIFY ASIMTUFII?
Do not receive ABILIFY ASIMTUFII if you are allergic to aripiprazole or any of the ingredients in ABILIFY ASIMTUFII. See the end of this Medication Guide for a complete list of ingredients in ABILIFY ASIMTUFII.

Before receiving ABILIFY ASIMTUFII, tell your healthcare provider about all of your medical conditions, including if you:

- have never taken aripiprazole before
- have or had diabetes or high blood sugar or a family history of diabetes or high blood sugar
- have or had high levels of total cholesterol, LDL cholesterol, or triglycerides, or low levels of HDL cholesterol
- have or had low or high blood pressure
- have or had heart problems or a stroke
- have or had a low white blood cell count
- have or had seizures (convulsions)
- have problems that may affect you receiving an injection in your buttocks
- are pregnant or plan to become pregnant. ABILIFY ASIMTUFII may harm your unborn baby. Receiving ABILIFY ASIMTUFII during your third trimester of pregnancy may cause your baby to have abnormal muscle movements or withdrawal symptoms after birth. Talk to your healthcare provider about the risk to your unborn baby if you receive ABILIFY ASIMTUFII during pregnancy.
  - Tell your healthcare provider right away if you become pregnant or think that you are pregnant during treatment with ABILIFY ASIMTUFII.
  - If you become pregnant during treatment with ABILIFY ASIMTUFII, talk to your healthcare provider about registering with the National Pregnancy Registry for Atypical Antipsychotics. You can register by calling 1-866-961-2388 or visit http://womensmentalhealth.org/clinical-and-research-programs/pregnancyregistry/.
- are breastfeeding or plan to breastfeed. ABILIFY ASIMTUFII can pass into your breast milk and it is not known if it may harm your baby. Talk to your healthcare provider about the best way to feed your baby during treatment with ABILIFY ASIMTUFII.

Tell your healthcare provider about all the medicines you take, including prescription medicines and over-the-counter medicines, vitamins, and herbal supplements.
ABILIFY ASIMTUFII and other medicines may affect each other causing possible serious side effects. ABILIFY ASIMTUFII may affect the way other medicines work, and other medicines may affect how ABILIFY ASIMTUFII works.
Your healthcare provider can tell you if it is safe to receive ABILIFY ASIMTUFII with your other medicines. Do not start or stop any medicines during treatment with ABILIFY ASIMTUFII without first talking to your healthcare provider.
Know the medicines you take. Keep a list of them to show your healthcare provider and pharmacist when you get a new medicine.

How should I receive ABILIFY ASIMTUFII?

- Follow your ABILIFY ASIMTUFII treatment schedule exactly as your healthcare provider tells you to.
- Your healthcare provider will tell you how much ABILIFY ASIMTUFII you will receive and when you will receive it.
- ABILIFY ASIMTUFII is an injection given only in your buttock by your healthcare provider 1 time every 2 months.
- There are 2 ways to start (initiate) treatment with ABILIFY ASIMTUFII if you currently take an antipsychotic medicine by mouth (oral):
  - 1-day initiation: You will receive 1 injection of ABILIFY ASIMTUFII in your buttock and 1 injection of Abilify Maintena in your arm or other buttock on your first day of treatment. You will also take 1 dose of aripiprazole by mouth.
    OR
  - 14-day initiation: You will receive 1 injection of ABILIFY ASIMTUFII in your buttock. You will also continue to take your oral aripiprazole or your current antipsychotic medicine by mouth for 14 days in a row.
- If you are already treated with Abilify Maintena you will receive 1 injection of ABILIFY ASIMTUFII instead of your next dose of Abilify Maintena and then you will receive ABILIFY ASIMTUFII 1 time every 2 months thereafter.
- You should not miss a dose of ABILIFY ASIMTUFII. If you miss a dose for some reason, call your healthcare provider right away to discuss what you should do next.

What should I avoid while receiving ABILIFY ASIMTUFII?

- Do not drive a car, operate machinery, or do other dangerous activities until you know how ABILIFY ASIMTUFII affects you. ABILIFY ASIMTUFII may affect your judgement, thinking or motor skills.
- Do not drink alcohol during treatment with ABILIFY ASIMTUFII.
- Do not become too hot or dehydrated during treatment with ABILIFY ASIMTUFII.
  - Do not exercise too much.
  - In hot weather, stay inside in a cool place if possible.
  - Stay out of the sun.
  - Do not wear too much clothing or heavy clothing.
  - Drink plenty of water.

What are the possible side effects of ABILIFY ASIMTUFII?
ABILIFY ASIMTUFII may cause serious side effects, including:

- See "What is the most important information I should know about ABILIFY ASIMTUFII?"
- Stroke, (cerebrovascular problems) in elderly people with dementia-related psychosis that can lead to death.
- Neuroleptic malignant syndrome (NMS), a serious condition that can lead to death. Call your healthcare provider or go to the nearest emergency room right away if you have some or all of the following signs and symptoms of NMS:

- high fever
- confusion
- changes in pulse, heart rate, and blood pressure

- stiff muscles
- increased sweating

- Uncontrolled body movements (tardive dyskinesia). ABILIFY ASIMTUFII may cause movements that you cannot control in your face, tongue, or other body parts. Tardive dyskinesia may not go away, even if you stop receiving ABILIFY ASIMTUFII. Tardive dyskinesia may also start after you stop receiving ABILIFY ASIMTUFII.
- Problems with your metabolism such as:

- high blood sugar (hyperglycemia) and diabetes: Increases in blood sugar can happen in some people who are treated with ABILIFY ASIMTUFII. Extremely high blood sugar can lead to coma or death. If you have diabetes or risk factors for diabetes such as being overweight, or a family history of diabetes, your healthcare provider should check your blood sugar before you start treatment with ABILIFY ASIMTUFII, and during treatment with ABILIFY ASIMTUFII.
  Call your healthcare provider if you have any of these symptoms of high blood sugar during treatment with ABILIFY ASIMTUFII:

- feel very thirsty
- feel very hungry
- feel sick to your stomach

- need to urinate more than usual
- feel weak or tired
- feel confused, or your breath smells fruity

- Increased fat levels (cholesterol and triglycerides) in your blood.
- Weight gain. You and your healthcare provider should check your weight regularly during treatment with ABILIFY ASIMTUFII.

- Unusual and uncontrollable (compulsive) urges. Some people receiving ABILIFY ASIMTUFII have had unusual strong urges to gamble and gambling that cannot be controlled (compulsive gambling). Other compulsive urges including sexual urges, shopping, and eating or binge eating. If you or your family members notice that you are having unusual urges or behaviors, talk to your healthcare provider.
- Decreased blood pressure (orthostatic hypotension). You may feel lightheaded or faint when you rise too quickly from a sitting or lying position.
- Falls. ABILIFY ASIMTUFII may make you sleepy or dizzy, may cause a decrease in your blood pressure when changing position (orthostatic hypotension), and can slow your thinking and motor skills which may lead to falls that can cause fractures or other injuries.
- Low white blood cell count. Your healthcare provider may do blood tests during your first few months of treatment with ABILIFY ASIMTUFII.
- Seizures (convulsions)
- Sleepiness, drowsiness, feeling tired, difficulty thinking and doing normal activities. See "What should I avoid while receiving ABILIFY ASIMTUFII?"
- Problems controlling your body temperature so that you feel too warm. See "What should I avoid while receiving ABILIFY ASIMTUFII?"
- Difficulty swallowing that can cause food or liquid to get into your lungs.

The most common side effects of ABILIFY ASIMTUFII include: weight gain, restlessness or feeling like you need to move (akathisia), injection site pain, or sleepiness (sedation).
These are not all the possible side effects of ABILIFY ASIMTUFII.
Call your doctor for medical advice about side effects. You may report side effects to FDA at 1-800-FDA-1088.

General information about the safe and effective use of ABILIFY ASIMTUFII.
If you would like more information, talk with your healthcare provider. You can ask your pharmacist or healthcare provider for information about ABILIFY ASIMTUFII that is written for healthcare professionals.

What are the ingredients in ABILIFY ASIMTUFII?
Active ingredient: aripiprazole monohydrate
Inactive ingredients: carboxymethylcellulose sodium, polyethylene glycol 400, povidone, sodium chloride, sodium phosphate monobasic monohydrate, sodium hydroxide and water for injection.
ABILIFY ASIMTUFII is a trademark of Otsuka Pharmaceutical Co., Ltd.
© 2025, Otsuka Pharmaceutical Co., Ltd., 2-9 Kanda-Tsukasamachi, Chiyoda-ku, Tokyo, 101-8535 Japan
For more information about ABILIFY ASIMTUFII, go to www.ABILIFYASIMTUFII.com or call 1-800-441-6763.

This Medication Guide has been approved by the U.S. Food and Drug Administration.

Revised: 03/2025

INSTRUCTIONS FOR USE

ABILIFY ASIMTUFII (a-BIL-i-fy AH-SIM-TUH-FYE)

(aripiprazole)

extended-release injectable suspension

The following information is intended for medical or healthcare professionals only and should be read by the medical or healthcare professional in conjunction with the full prescribing information.

- Read the complete instructions for preparation and administration below before administering ABILIFY ASIMTUFII.
- To be prepared and administered only by a healthcare professional once every two months.
- ABILIFY ASIMTUFII pre-filled syringe is single-dose only. Re-use may lead to infection or other illness/injury.
- For gluteal intramuscular injection only. Do not administer by any other route.
- Prior to administration, visually inspect ABILIFY ASIMTUFII pre-filled syringe for particulate matter and discoloration. The suspension should appear to be a uniform, homogeneous suspension that is opaque and milky-white in color. Do not use ABILIFY ASIMTUFII pre-filled syringe if the suspension is discolored, or particulate matter is present.

Contents of Kit

Each kit contains one sterile pre-filled syringe containing ABILIFY ASIMTUFII (aripiprazole) 720 mg or 960 mg extended-release injectable suspension and two safety needles:

- One sterile 1 ½ inch 22 gauge needle (in black packaging)
- One sterile 2 inch 21 gauge needle (in green packaging)

Preparation Prior to Administration

- Remove the ABILIFY ASIMTUFII pre-filled syringe from the package.
- Tap the syringe on your hand at least 10 (ten) times (Figure 1).
- After tapping, shake the syringe vigorously for at least 10 (ten) seconds until the medication is uniform (Figure 2).
  Figure 1
  Figure 2

Select the appropriate needle

Needle selection is determined by patient body type.

For gluteal intramuscular administration only.

- For non-obese patients - 22-gauge, 1.5-inch (38 mm) safety needle with needle protection device (needle in black packaging)
- For obese patients - 21-gauge, 2-inch (51 mm) safety needle with needle protection device (needle in green packaging)

Refer to Table 1 below for needle information:

Table 1: Needle Size Required by Body Type
Body Type |  | Needle Size | Needle Packaging Color
 | Non-obese | 1 ½ inch, 22 gauge | black
 | Obese | 2 inch, 21 gauge | green

Attach the needle

- Twist and pull off the pre-filled syringe tip-cap (Figure 3).
- While holding the base of the needle, ensure the needle is firmly seated on the safety device with a push. Gently twist clockwise until SECURELY fitted (Figure 3).

Figure 3

Expel Air

- When you are ready to administer the injection of ABILIFY ASIMTUFII, hold the pre-filled syringe upright and remove the needle-cap straight up (Figure 4). Do not twist the needle-cap, as this may loosen the needle from the syringe.

Figure 4

- Slowly advance the plunger rod upward to expel the air and until the suspension fills needle base (Figure 5).

Figure 5

Inject the dose

- Slowly inject the entire contents of the pre-filled syringe intramuscularly into the gluteal muscle of the patient (Figure 6).

Do not administer by any other route.

Do not massage the injection site.

Figure 6

Disposal Procedure

- After the injection, press the safety shield on a hard surface to cover and lock shield over the needle (Figure 7 and 8)
  Figure 7
  Figure 8
- Immediately discard used syringe and the unused needle in an approved sharps container (Figure 9).
- The unused needle should not be saved for future use.

Figure 9

PRINCIPAL DISPLAY PANEL - 720 mg/2.4 mL Syringe Carton

NDC 59148-102-80
Rx only

720 mg/2.4 mL
(300 mg/mL)

Abilify Asimtufii®
(aripiprazole) extended-release injectable suspension

FOR GLUTEAL INTRAMUSCULAR INJECTION ONLY

Contents: 1 single-dose prefilled syringe and 2 safety needles
(a 1 ½ inch, 22 G needle and a 2 inch, 21 G needle)

PRINCIPAL DISPLAY PANEL - 960 mg/3.2 mL Syringe Carton

NDC 59148-114-80
Rx only

960 mg/3.2 mL
(300 mg/mL)

Abilify Asimtufii®
(aripiprazole) extended-release injectable suspension

FOR GLUTEAL INTRAMUSCULAR INJECTION ONLY

Contents: 1 single-dose prefilled syringe and 2 safety needles
(a 1 ½ inch, 22 G needle and a 2 inch, 21 G needle)